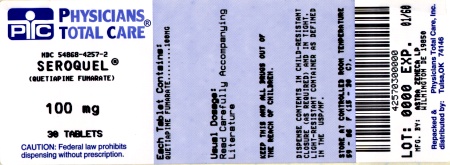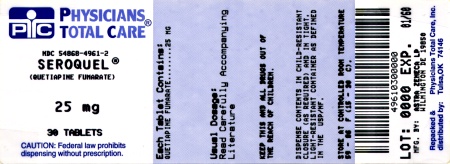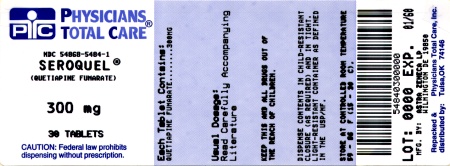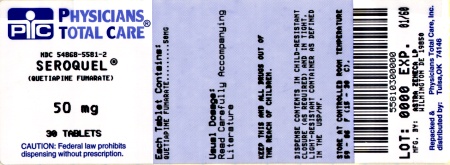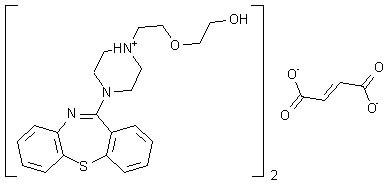 DRUG LABEL: SEROQUEL
NDC: 54868-4961 | Form: TABLET, FILM COATED
Manufacturer: Physicians Total Care, Inc.
Category: prescription | Type: HUMAN PRESCRIPTION DRUG LABEL
Date: 20120206

ACTIVE INGREDIENTS: QUETIAPINE FUMARATE 25 mg/1 1
INACTIVE INGREDIENTS: POVIDONE; DIBASIC CALCIUM PHOSPHATE DIHYDRATE; CELLULOSE, MICROCRYSTALLINE; SODIUM STARCH GLYCOLATE TYPE A POTATO; MAGNESIUM STEARATE; HYPROMELLOSES; POLYETHYLENE GLYCOL; TITANIUM DIOXIDE; FERRIC OXIDE RED; FERRIC OXIDE YELLOW; LACTOSE MONOHYDRATE; WATER

HIGHLIGHTS OF PRESCRIBING INFORMATION

These highlights do not include all the information needed to use SEROQUEL safely and effectively. See full prescribing information for SEROQUEL.
SEROQUEL® (quetiapine fumarate) Tablets
Initial U.S. Approval: 1997

WARNING: INCREASED MORTALITY IN ELDERLY PATIENTS WITH DEMENTIA-RELATED PSYCHOSIS See Full Prescribing Information for complete boxed warning.

- Antipsychotic drugs are associated with an increased risk of death (5.1)
- Quetiapine is not approved for elderly patients with Dementia-Related Psychosis (5.1)

SUICIDALITY AND ANTIDEPRESSANT DRUGS

WARNING: SUICIDALITY AND ANTIDEPRESSANT DRUGS See Full Prescribing Information for complete boxed warning.

- Increased risk of suicidal thinking and behavior in children, adolescents and young adults taking antidepressants for major depressive disorder and other psychiatric disorders (5.2)

Recent Major Changes

Warnings and Precautions, Hyperglycemia (5.4), 1/2011

Warnings and Precautions, Hyperlipidemia (5.5), 1/2011

Warnings and Precautions, Weight Gain (5.6), 1/2011

Warnings and Precautions, QT Prolongation, (5.12), 7/2011

Warnings and Precautions, Hypothyroidism (5.14), 1/2011

Warnings and Precautions, Withdrawal (5.23), 5/2010

1 INDICATIONS AND USAGE

SEROQUEL is an atypical antipsychotic indicated for the:

Treatment of schizophrenia (1.1)

- Adults: Efficacy was established in three 6–week clinical trials in patients with schizophrenia (14.1)
- Adolescents (ages 13–17): Efficacy was established in one 6–week trial in patients with schizophrenia (14.1)

Acute treatment of manic episodes associated with bipolar I disorder, both as monotherapy and as an adjunct to lithium or divalproex (1.2)

- Adults: Efficacy was established in two 12–week monotherapy trials and in one 3–week adjunctive trial in patients with manic episodes associated with bipolar I disorder (14.2)
- Children and Adolescents (ages 10–17): Efficacy was established in one 3–week monotherapy trial in patients with manic episodes associated with bipolar I disorder (14.2)

Acute treatment of depressive episodes associated with bipolar disorder (1.2)

- Adults: Efficacy was established in two 8–week trials in patients with bipolar I or II disorder (14.2)

Maintenance treatment of bipolar I disorder as an adjunct to lithium or divalproex (1.2)

- Adults: Efficacy was established in two maintenance trials in adults (14.2)

2 DOSAGE AND ADMINISTRATION

SEROQUEL can be taken with or without food.

Indication | Dosing Instructions | Recommended Dose/Dose Range
Schizophrenia-Adults (2.1) | Day 1: 25 mg twice daily. Increase in increments of 25 mg-50 mg divided two or three times on Days 2 and 3 to range of 300-400 mg by Day 4. Further adjustments can be made in increments of 25–50 mg twice a day, in intervals of not less than 2 days. | 150-750 mg/day
Schizophrenia- Adolescents (13-17 years) (2.1) | Day 1: 25 mg twice daily.; Day 2: Twice daily dosing totaling 100 mg.; Day 3: Twice daily dosing totaling 200 mg.; Day 4: Twice daily dosing totaling 300 mg.; Day 5: Twice daily dosing totaling 400 mg.; Further adjustments should be in increments no greater than 100 mg/day within the recommended dose range of 400-800 mg/day. Based on response and tolerability, may be administered three times daily. | 400-800 mg/day
Bipolar Mania- Adults Monotherapy or as an adjunct to lithium or divalproex (2.2) | Day 1: Twice daily dosing totaling 100 mg.; Day 2: Twice daily dosing totaling 200 mg.; Day 3: Twice daily dosing totaling 300 mg.; Day 4: Twice daily dosing totaling 400 mg.; Further dosage adjustments up to 800 mg/day by Day 6 should be in increments of no greater than 200 mg/day. | 400-800 mg/day
Bipolar Mania- Children and Adolescents (10 to 17 years), Monotherapy | Day 1: 25 mg twice daily.; Day 2: Twice daily dosing totaling 100 mg.; Day 3: Twice daily dosing totaling 200 mg.; Day 4: Twice daily dosing totaling 300 mg.; Day 5: Twice daily dosing totaling 400 mg.; Further adjustments should be in increments no greater than 100 mg/day within the recommended dose range of 400-600 mg/day. Based on response and tolerability, may be administered three times daily. | 400-600 mg/day
Bipolar Depression- Adults | Administer once daily at bedtime.; Day 1: 50 mg.; Day 2: 100 mg.; Day 3: 200 mg.; Day 4: 300 mg. | 300 mg/day
Bipolar I Disorder Maintenance Therapy- Adults | Administer twice daily totaling 400-800 mg/day as adjunct to lithium or divalproex. Generally, in the maintenance phase, patients continued on the same dose on which they were stabilized.

3 DOSAGE FORMS AND STRENGTHS

25 mg, 50 mg, 100 mg, 200 mg, 300 mg, and 400 mg (3)

4 CONTRAINDICATIONS

None (4)

5 WARNINGS AND PRECAUTIONS

- Increased Mortality in Elderly Patients with Dementia-Related Psychosis: Atypical antipsychotic drugs, including quetiapine, are associated with an increased risk of death; causes of death are variable. (5.1)
- Suicidality and Antidepressant Drugs: Increased the risk of suicidal thinking and behavior in children, adolescents and young adults taking antidepressants for major depressive disorder and other psychiatric disorders. (5.2)
- Neuroleptic Malignant Syndrome (NMS): Manage with immediate discontinuation and close monitoring. (5.3)
- Hyperglycemia and Diabetes Mellitus (DM): Ketoacidosis, hyperosmolar coma and death have been reported in patients treated with atypical antipsychotics, including quetiapine. Any patient treated with atypical antipsychotics should be monitored for symptoms of hyperglycemia including polydipsia, polyuria, polyphagia, and weakness. When starting treatment, patients with diabetes or risk factors for diabetes should undergo blood glucose testing before and during treatment. (5.4)
- Hyperlipidemia: Undesirable alterations in lipids have been observed. Increases in total cholesterol, LDL-cholesterol and triglycerides and decreases in HDL-cholesterol have been reported in clinical trials. Appropriate clinical monitoring is recommended, including fasting blood lipid testing at the beginning of, and periodically during treatment. (5.5)
- Weight Gain: Patients should receive regular monitoring of weight. (5.6)
- Tardive Dyskinesia: Discontinue if clinically appropriate. (5.7)
- Orthostatic Hypotension: Associated dizziness, tachycardia and syncope may occur especially during the initial dose titration period. (5.8)
- Increased Blood Pressure in Children and Adolescents: Blood pressure should be measured at the beginning of, and periodically during treatment in children and adolescents. (5.9)
- Leukopenia, Neutropenia and Agranulocytosis have been reported with atypical antipsychotics including SEROQUEL. Patients with a pre-existing low white cell count (WBC) or a history of leukopenia/neutropenia should have complete blood count (CBC) monitored frequently during the first few months of treatment and should discontinue SEROQUEL at the first sign of a decline in WBC in absence of other causative factors. (5.10)
- Cataracts: Lens changes have been observed in patients during long-term quetiapine treatment. Lens examination is recommended when starting treatment and at 6-month intervals during chronic treatment. (5.11)
- QT Prolongation: Post-marketing cases show increases in QT interval in patients who overdosed on quetiapine, in patients with concomitant illness, and in patients taking medicines known to cause electrolyte imbalance or increase QT interval. Avoid use with drugs that increase the QT interval and in patients with risk factors for prolonged QT interval. (5.12)
- Suicide: The possibility of a suicide attempt is inherent in schizophrenia and bipolar disorder, and close supervision of high risk patients should accompany drug therapy. (5.21)
- See Full Prescribing Information for additional WARNINGS and PRECAUTIONS.

6 ADVERSE REACTIONS

Most common adverse reactions (incidence ≥5% and twice placebo): Adults: somnolence, dry mouth, dizziness, constipation, asthenia, abdominal pain, postural hypotension, pharyngitis, weight gain, lethargy, ALT increased, dyspepsia. (6.1)

Children and Adolescents: somnolence, dizziness, fatigue, increased appetite, nausea, vomiting, dry mouth, tachycardia, weight increased. (6.1)

To report SUSPECTED ADVERSE REACTIONS, contact AstraZeneca at 1-800-236-9933 or FDA at 1-800-FDA-1088 or www.fda.gov/medwatch.

7 DRUG INTERACTIONS

- P450 3A Inhibitors: May decrease the clearance of quetiapine. Lower doses of quetiapine may be required. (7.1)
- Hepatic Enzyme Inducers: May increase the clearance of quetiapine. Higher doses of quetiapine may be required with phenytoin or other inducers. (7.1)
- Centrally Acting Drugs: Caution should be used when quetiapine is used in combination with other CNS acting drugs. (7)
- Antihypertensive Agents: Quetiapine may add to the hypotensive effects of these agents. (7)
- Levodopa and Dopamine Agents: Quetiapine may antagonize the effect of these drugs. (7)
- Drugs known to cause electrolyte imbalance or increase QT interval: Caution should be used when quetiapine is used concomitantly with these drugs. (7)
- Interference with Urine Drug Screens: False positive urine drug screens using immunoassays for methadone or tricyclic antidepressants (TCAs) in patients taking quetiapine have been reported. (7).

8 USE IN SPECIFIC POPULATIONS

- Geriatric Use: Consider a lower starting dose (50 mg/day), slower titration, and careful monitoring during the initial dosing period. (8.5)
- Hepatic Impairment: Lower starting doses (25 mg/day) and slower titration may be needed. (2.3, 12.3)
- Pregnancy: Limited human data. Based on animal data, may cause fetal harm. Quetiapine should be used only if the potential benefit justifies the potential risk. (8.1)
- Nursing Mothers: Breastfeeding is not recommended. (8.3)
- Pediatric Use: Safety and effectiveness has only been established for schizophrenia in adolescent patients 13 to 17 years of age and in bipolar mania in children and adolescent patients 10 to 17 years of age. (8.4)

FULL PRESCRIBING INFORMATION

WARNING: INCREASED MORTALITY IN ELDERLY PATIENTS WITH DEMENTIA-RELATED PSYCHOSIS

Elderly patients with dementia-related psychosis treated with antipsychotic drugs are at an increased risk of death. Analyses of seventeen placebo-controlled trials (modal duration of 10 weeks) largely in patients taking atypical antipsychotic drugs, revealed a risk of death in drug-treated patients of between 1.6 to 1.7 times the risk of death in placebo-treated patients. Over the course of a typical 10-week controlled trial, the rate of death in drug-treated patients was about 4.5%, compared to a rate of about 2.6% in the placebo group. Although the causes of death were varied, most of the deaths appeared to be either cardiovascular (e.g., heart failure, sudden death) or infectious (e.g., pneumonia) in nature. Observational studies suggest that, similar to atypical antipsychotic drugs, treatment with conventional antipsychotic drugs may increase mortality. The extent to which the findings of increased mortality in observational studies may be attributed to the antipsychotic drug as opposed to some characteristic(s) of the patients is not clear. SEROQUEL (quetiapine) is not approved for the treatment of patients with dementia-related psychosis [see Warnings and Precautions (5.1)].

SUICIDALITY AND ANTIDEPRESSANT DRUGS

Antidepressants increased the risk compared to placebo of suicidal thinking and behavior (suicidality) in children, adolescents, and young adults in short-term studies of major depressive disorder (MDD) and other psychiatric disorders. Anyone considering the use of SEROQUEL or any other antidepressant in a child, adolescent, or young adult must balance this risk with the clinical need. Short-term studies did not show an increase in the risk of suicidality with antidepressants compared to placebo in adults beyond age 24; there was a reduction in risk with antidepressants compared to placebo in adults aged 65 and older. Depression and certain other psychiatric disorders are themselves associated with increases in the risk of suicide. Patients of all ages who are started on antidepressant therapy should be monitored appropriately and observed closely for clinical worsening, suicidality, or unusual changes in behavior. Families and caregivers should be advised of the need for close observation and communication with the prescriber. SEROQUEL is not approved for use in patients under ten years of age [see Warnings and Precautions (5.2)].

1 INDICATIONS AND USAGE

1.1 Schizophrenia

SEROQUEL is indicated for the treatment of schizophrenia. The efficacy of SEROQUEL in schizophrenia was established in three 6-week trials in adults and one 6–week trial in adolescents (13–17 years). The effectiveness of SEROQUEL for the maintenance treatment of schizophrenia has not been systematically evaluated in controlled clinical trials [see Clinical Studies (14.1)].

1.2 Bipolar Disorder

SEROQUEL is indicated for the acute treatment of manic episodes associated with bipolar I disorder, both as monotherapy and as an adjunct to lithium or divalproex. Efficacy was established in two 12-week monotherapy trials in adults, in one 3-week adjunctive trial in adults, and in one 3-week monotherapy trial in pediatric patients (10-17 years) [see Clinical Studies (14.2)].

SEROQUEL is indicated as monotherapy for the acute treatment of depressive episodes associated with bipolar disorder. Efficacy was established in two 8-week monotherapy trials in adult patients with bipolar I and bipolar II disorder [see Clinical Studies (14.2)].

SEROQUEL is indicated for the maintenance treatment of bipolar I disorder, as an adjunct to lithium or divalproex. Efficacy was established in two maintenance trials in adults. The effectiveness of SEROQUEL as monotherapy for the maintenance treatment of bipolar disorder has not been systematically evaluated in controlled clinical trials [see Clinical Studies (14.2)].

1.3 Special Considerations in Treating Pediatric Schizophrenia and Bipolar I Disorder

Pediatric schizophrenia and bipolar I disorder are serious mental disorders, however, diagnosis can be challenging. For pediatric schizophrenia, symptom profiles can be variable, and for bipolar I disorder, patients may have variable patterns of periodicity of manic or mixed symptoms. It is recommended that medication therapy for pediatric schizophrenia and bipolar I disorder be initiated only after a thorough diagnostic evaluation has been performed and careful consideration given to the risks associated with medication treatment. Medication treatment for both pediatric schizophrenia and bipolar I disorder is indicated as part of a total treatment program that often includes psychological, educational and social interventions.

2 DOSAGE AND ADMINISTRATION

SEROQUEL can be taken with or without food.

2.1 Schizophrenia

Adults

Dose Selection— SEROQUEL should generally be administered with an initial dose of 25 mg twice daily, with increases in total daily dose of 25 mg - 50 mg divided in two or three doses on the second and third day, as tolerated, to a total dose range of 300 mg to 400 mg daily by the fourth day. Further dosage adjustments, if indicated, should generally occur at intervals of not less than 2 days, as steady-state for SEROQUEL would not be achieved for approximately 1-2 days in the typical patient. When dosage adjustments are necessary, dose increments/decrements of 25 mg - 50 mg divided twice daily are recommended. Most efficacy data with SEROQUEL were obtained using three times daily dosing regimens, but in one controlled trial 225 mg given twice per day was also effective.

Efficacy in schizophrenia was demonstrated in a dose range of 150 mg/day to 750 mg/day in the clinical trials supporting the effectiveness of SEROQUEL. In a dose response study, doses above 300 mg/day were not demonstrated to be more efficacious than the 300 mg/day dose. In other studies, however, doses in the range of 400 mg/day - 500 mg/day appeared to be needed. The safety of doses above 800 mg/day has not been evaluated in clinical trials.

Maintenance Treatment—The effectiveness of SEROQUEL for longer than 6 weeks has not been evaluated in controlled clinical trials. While there is no body of evidence available to answer the question of how long the patient treated with SEROQUEL should be maintained, it is generally recommended that responding patients be continued beyond the acute response, but at the lowest dose needed to maintain remission. Patients should be periodically reassessed to determine the need for maintenance treatment.

Adolescents (13-17 years)

Dose Selection—SEROQUEL should be administered twice daily. However, based on response and tolerability SEROQUEL may be administered three times daily where needed.

The total daily dose for the initial five days of therapy is 50 mg (Day 1), 100 mg (Day 2), 200 mg (Day 3), 300 mg (Day 4) and 400 mg (Day 5). After Day 5, the dose should be adjusted within the recommended dose range of 400 mg/day to 800 mg/day based on response and tolerability. Dosage adjustments should be in increments of no greater than 100 mg/day. Efficacy was demonstrated with SEROQUEL at both 400 mg and 800 mg; however, no additional benefit was seen in the 800 mg group.

Maintenance Treatment—The effectiveness of SEROQUEL for longer than 6 weeks has not been evaluated in controlled clinical trials. While there is no body of evidence available to answer the question of how long the patient treated with SEROQUEL should be maintained, it is generally recommended that responding patients be continued beyond the acute response, but at the lowest dose needed to maintain remission. Patients should be periodically reassessed to determine the need for maintenance treatment.

2.2 Bipolar Disorder

Adults

Acute Treatment of Manic Episodes in Bipolar I Disorder

Dose Selection—When used as monotherapy or adjunct therapy (with lithium or divalproex), SEROQUEL should be initiated in twice daily doses totaling 100 mg/day on Day 1, increased to 400 mg/day on Day 4 in increments of up to 100 mg/day in twice daily divided doses. Further dosage adjustments up to 800 mg/day by Day 6 should be in increments of no greater than 200 mg/day. Data indicate that the majority of patients responded between 400 mg/day to 800 mg/day. The safety of doses above 800 mg/day has not been evaluated in clinical trials.

Acute Treatment of Depressive Episodes in Bipolar Disorder

Dose Selection—SEROQUEL should be administered once daily at bedtime to reach 300 mg/day by Day 4.

Recommended Dosing Schedule
Day | Day 1 | Day 2 | Day 3 | Day 4
SEROQUEL | 50 mg | 100 mg | 200 mg | 300 mg

In the clinical trials supporting effectiveness, the dosing schedule was 50 mg, 100 mg, 200 mg and 300 mg/day for Days 1-4 respectively. Patients receiving 600 mg increased to 400 mg on Day 5 and 600 mg on Day 8 (Week 1). Antidepressant efficacy was demonstrated with SEROQUEL at both 300 mg and 600 mg; however, no additional benefit was seen in the 600 mg group.

Maintenance Treatment of Bipolar I Disorder

Maintenance of efficacy in bipolar I disorder was demonstrated with SEROQUEL (administered twice daily totaling 400 to 800 mg per day) as adjunct therapy to lithium or divalproex. Generally, in the maintenance phase, patients continued on the same dose on which they were stabilized during the stabilization phase [see Clinical Studies (14.2)].

Children and Adolescents (10 to 17 years)

Acute Treatment of Manic Episodes in Bipolar I Disorder

Dose Selection—SEROQUEL should be administered twice daily. However, based on response and tolerability SEROQUEL may be administered three times daily where needed.

The total daily dose for the initial five days of therapy is 50 mg (Day 1), 100 mg (Day 2), 200 mg (Day 3), 300 mg (Day 4) and 400 mg (Day 5). After Day 5, the dose should be adjusted within the recommended dose range of 400 to 600 mg/day based on response and tolerability. Dosage adjustments should be in increments of no greater than 100 mg/day. Efficacy was demonstrated with SEROQUEL at both 400 mg and 600 mg; however, no additional benefit was seen in the 600 mg group.

Maintenance Treatment of Bipolar I Disorder

The effectiveness of SEROQUEL for longer than 3 weeks has not been evaluated in controlled clinical trials of children and adolescents. While there is no body of evidence available to answer the question of how long the patient treated with SEROQUEL should be maintained, it is generally recommended that responding patients be continued beyond the acute response, but at the lowest dose needed to maintain remission. Patients should be periodically reassessed to determine the need for maintenance treatment.

2.3 Dosing in Special Populations

Consideration should be given to a slower rate of dose titration and a lower target dose in the elderly and in patients who are debilitated or who have a predisposition to hypotensive reactions [see Clinical Pharmacology (12)]. When indicated, dose escalation should be performed with caution in these patients.

Patients with hepatic impairment should be started on 25 mg/day. The dose should be increased daily in increments of 25 mg/day – 50 mg/day to an effective dose, depending on the clinical response and tolerability of the patient.

2.4 Reinitiation of Treatment in Patients Previously Discontinued

Although there are no data to specifically address reinitiation of treatment, it is recommended that when restarting patients who have had an interval of less than one week off SEROQUEL, titration of SEROQUEL is not required and the maintenance dose may be reinitiated. When restarting therapy of patients who have been off SEROQUEL for more than one week, the initial titration schedule should be followed.

2.5 Switching from Antipsychotics

There are no systematically collected data to specifically address switching patients with schizophrenia from antipsychotics to SEROQUEL, or concerning concomitant administration with antipsychotics. While immediate discontinuation of the previous antipsychotic treatment may be acceptable for some patients with schizophrenia, more gradual discontinuation may be most appropriate for others. In all cases, the period of overlapping antipsychotic administration should be minimized. When switching patients with schizophrenia from depot antipsychotics, if medically appropriate, initiate SEROQUEL therapy in place of the next scheduled injection. The need for continuing existing EPS medication should be re-evaluated periodically.

3 DOSAGE FORMS AND STRENGTHS

25 mg tablets

50 mg tablets

100 mg tablets

200 mg tablets

300 mg tablets

400 mg tablets

4 CONTRAINDICATIONS

None known

5 WARNINGS AND PRECAUTIONS

5.1 Increased Mortality in Elderly Patients with Dementia-Related Psychosis

Elderly patients with dementia-related psychosis treated with antipsychotic drugs are at an increased risk of death. SEROQUEL (quetiapine fumarate) is not approved for the treatment of patients with dementia-related psychosis

(see Boxed Warning).

5.2 Clinical Worsening and Suicide Risk

Patients with major depressive disorder (MDD), both adult and pediatric, may experience worsening of their depression and/or the emergence of suicidal ideation and behavior (suicidality) or unusual changes in behavior, whether or not they are taking antidepressant medications, and this risk may persist until significant remission occurs. Suicide is a known risk of depression and certain other psychiatric disorders, and these disorders themselves are the strongest predictors of suicide. There has been a long-standing concern, however, that antidepressants may have a role in inducing worsening of depression and the emergence of suicidality in certain patients during the early phases of treatment. Pooled analyses of short-term placebo-controlled trials of antidepressant drugs (SSRIs and others) showed that these drugs increase the risk of suicidal thinking and behavior (suicidality) in children, adolescents, and young adults (ages 18-24) with major depressive disorder (MDD) and other psychiatric disorders. Short-term studies did not show an increase in the risk of suicidality with antidepressants compared to placebo in adults beyond age 24; there was a reduction with antidepressants compared to placebo in adults aged 65 and older.

The pooled analyses of placebo-controlled trials in children and adolescents with MDD, obsessive compulsive disorder (OCD), or other psychiatric disorders included a total of 24 short-term trials of 9 antidepressant drugs in over 4400 patients. The pooled analyses of placebo-controlled trials in adults with MDD or other psychiatric disorders included a total of 295 short-term trials (median duration of 2 months) of 11 antidepressant drugs in over 77,000 patients. There was considerable variation in risk of suicidality among drugs, but a tendency toward an increase in the younger patients for almost all drugs studied. There were differences in absolute risk of suicidality across the different indications, with the highest incidence in MDD. The risk differences (drug vs. placebo), however, were relatively stable within age strata and across indications. These risk differences (drug-placebo difference in the number of cases of suicidality per 1000 patients treated) are provided in Table 1.

Table 1
Age Range | Drug-Placebo Difference in Number of Cases of Suicidality per 1000 Patients Treated
 | Increases Compared to Placebo
<18 | 14 additional cases
18–24 | 5 additional cases
 | Decreases Compared to Placebo
25–64 | 1 fewer case
≥65 | 6 fewer cases

No suicides occurred in any of the pediatric trials. There were suicides in the adult trials, but the number was not sufficient to reach any conclusion about drug effect on suicide.

It is unknown whether the suicidality risk extends to longer-term use, i.e., beyond several months. However, there is substantial evidence from placebo-controlled maintenance trials in adults with depression that the use of antidepressants can delay the recurrence of depression.

All patients being treated with antidepressants for any indication should be monitored appropriately and observed closely for clinical worsening, suicidality, and unusual changes in behavior, especially during the initial few months of a course of drug therapy, or at times of dose changes, either increases or decreases.

The following symptoms, anxiety, agitation, panic attacks, insomnia, irritability, hostility, aggressiveness, impulsivity, akathisia (psychomotor restlessness), hypomania, and mania, have been reported in adult and pediatric patients being treated with antidepressants for major depressive disorder as well as for other indications, both psychiatric and nonpsychiatric. Although a causal link between the emergence of such symptoms and either the worsening of depression and/or the emergence of suicidal impulses has not been established, there is concern that such symptoms may represent precursors to emerging suicidality.

Consideration should be given to changing the therapeutic regimen, including possibly discontinuing the medication, in patients whose depression is persistently worse, or who are experiencing emergent suicidality or symptoms that might be precursors to worsening depression or suicidality, especially if these symptoms are severe, abrupt in onset, or were not part of the patient's presenting symptoms.

Families and caregivers of patients being treated with antidepressants for major depressive disorder or other indications, both psychiatric and nonpsychiatric, should be alerted about the need to monitor patients for the emergence of agitation, irritability, unusual changes in behavior, and the other symptoms described above, as well as the emergence of suicidality, and to report such symptoms immediately to healthcare providers. Such monitoring should include daily observation by families and caregivers. Prescriptions for SEROQUEL should be written for the smallest quantity of tablets consistent with good patient management, in order to reduce the risk of overdose.

Screening Patients for Bipolar Disorder: A major depressive episode may be the initial presentation of bipolar disorder. It is generally believed (though not established in controlled trials) that treating such an episode with an antidepressant alone may increase the likelihood of precipitation of a mixed/manic episode in patients at risk for bipolar disorder. Whether any of the symptoms described above represent such a conversion is unknown. However, prior to initiating treatment with an antidepressant, patients with depressive symptoms should be adequately screened to determine if they are at risk for bipolar disorder; such screening should include a detailed psychiatric history, including a family history of suicide, bipolar disorder, and depression. It should be noted that SEROQUEL is approved for use in treating adult bipolar depression.

5.3 Neuroleptic Malignant Syndrome (NMS)

A potentially fatal symptom complex sometimes referred to as Neuroleptic Malignant Syndrome (NMS) has been reported in association with administration of antipsychotic drugs, including SEROQUEL. Rare cases of NMS have been reported with SEROQUEL. Clinical manifestations of NMS are hyperpyrexia, muscle rigidity, altered mental status, and evidence of autonomic instability (irregular pulse or blood pressure, tachycardia, diaphoresis, and cardiac dysrhythmia). Additional signs may include elevated creatine phosphokinase, myoglobinuria (rhabdomyolysis) and acute renal failure.

The diagnostic evaluation of patients with this syndrome is complicated. In arriving at a diagnosis, it is important to exclude cases where the clinical presentation includes both serious medical illness (e.g., pneumonia, systemic infection, etc.) and untreated or inadequately treated extrapyramidal signs and symptoms (EPS). Other important considerations in the differential diagnosis include central anticholinergic toxicity, heat stroke, drug fever and primary central nervous system (CNS) pathology.

The management of NMS should include: 1) immediate discontinuation of antipsychotic drugs and other drugs not essential to concurrent therapy; 2) intensive symptomatic treatment and medical monitoring; and 3) treatment of any concomitant serious medical problems for which specific treatments are available. There is no general agreement about specific pharmacological treatment regimens for NMS.

If a patient requires antipsychotic drug treatment after recovery from NMS, the potential reintroduction of drug therapy should be carefully considered. The patient should be carefully monitored since recurrences of NMS have been reported.

5.4 Hyperglycemia and Diabetes Mellitus

Hyperglycemia, in some cases extreme and associated with ketoacidosis or hyperosmolar coma or death, has been reported in patients treated with atypical antipsychotics, including quetiapine. Assessment of the relationship between atypical antipsychotic use and glucose abnormalities is complicated by the possibility of an increased background risk of diabetes mellitus in patients with schizophrenia and the increasing incidence of diabetes mellitus in the general population. Given these confounders, the relationship between atypical antipsychotic use and hyperglycemia-related adverse reactions is not completely understood. However, epidemiological studies suggest an increased risk of treatment-emergent hyperglycemia-related adverse reactions in patients treated with the atypical antipsychotics. Precise risk estimates for hyperglycemia-related adverse reactions in patients treated with atypical antipsychotics are not available.

Patients with an established diagnosis of diabetes mellitus who are started on atypical antipsychotics should be monitored regularly for worsening of glucose control. Patients with risk factors for diabetes mellitus (e.g., obesity, family history of diabetes) who are starting treatment with atypical antipsychotics should undergo fasting blood glucose testing at the beginning of treatment and periodically during treatment.

Any patient treated with atypical antipsychotics should be monitored for symptoms of hyperglycemia including polydipsia, polyuria, polyphagia, and weakness. Patients who develop symptoms of hyperglycemia during treatment with atypical antipsychotics should undergo fasting blood glucose testing. In some cases, hyperglycemia has resolved when the atypical antipsychotic was discontinued; however, some patients required continuation of anti-diabetic treatment despite discontinuation of the suspect drug.

In some patients, a worsening of more than one of the metabolic parameters of weight, blood glucose and lipids was observed in clinical studies. Changes in these parameters should be managed as clinically appropriate.

Adults:

Table 2: Fasting Glucose — Proportion of Patients Shifting to ≥ 126 mg/dL in Short-Term (≤ 12 weeks) Placebo-Controlled Studies
Laboratory Analyte | Category Change (At Least Once) from Baseline | Treatment Arm | N | Patients n (%)
Fasting Glucose | Normal to High (<100 mg/dL to ≥ 126 mg/dL) | Quetiapine | 2907 | 71 (2.4%)
Fasting Glucose | Normal to High (<100 mg/dL to ≥ 126 mg/dL) | Placebo | 1346 | 19 (1.4%)
Fasting Glucose | Borderline to High (≥ 100 mg/dL and < 126 mg/dL to ≥ 126 mg/dL) | Quetiapine | 572 | 67 (11.7%)
Fasting Glucose | Borderline to High (≥ 100 mg/dL and < 126 mg/dL to ≥ 126 mg/dL) | Placebo | 279 | 33 (11.8%)

In a 24-week trial (active-controlled, 115 patients treated with SEROQUEL) designed to evaluate glycemic status with oral glucose tolerance testing of all patients, at week 24 the incidence of a treatment-emergent post-glucose challenge glucose level ≥ 200 mg/dL was 1.7% and the incidence of a fasting treatment-emergent blood glucose level ≥ 126 mg/dL was 2.6%. The mean change in fasting glucose from baseline was 3.2 mg/dL and mean change in 2 hour glucose from baseline was -1.8 mg/dL for quetiapine.

In 2 long-term placebo-controlled randomized withdrawal clinical trials for bipolar maintenance, mean exposure of 213 days for SEROQUEL (646 patients) and 152 days for placebo (680 patients), the mean change in glucose from baseline was +5.0 mg/dL for SEROQUEL and –0.05 mg/dL for placebo. The exposure-adjusted rate of any increased blood glucose level (≥ 126 mg/dL) for patients more than 8 hours since a meal (however, some patients may not have been precluded from calorie intake from fluids during fasting period) was 18.0 per 100 patient years for SEROQUEL (10.7% of patients; n=556) and 9.5 for placebo per 100 patient years (4.6% of patients; n=581).

Children and Adolescents: In a placebo-controlled SEROQUEL monotherapy study of adolescent patients (13 –17 years of age) with schizophrenia (6 weeks duration), the mean change in fasting glucose levels for SEROQUEL (n=138) compared to placebo (n=67) was –0.75 mg/dL versus –1.70 mg/dL. In a placebo-controlled SEROQUEL monotherapy study of children and adolescent patients (10 –17 years of age) with bipolar mania (3 weeks duration), the mean change in fasting glucose level for SEROQUEL (n=170) compared to placebo (n=81) was 3.62 mg/dL versus –1.17 mg/dL. No patient in either study with a baseline normal fasting glucose level (<100 mg/dL) or a baseline borderline fasting glucose level (≥100 mg/dL and <126 mg/dL) had a treatment-emergent blood glucose level of ≥126 mg/dL.

5.5 Hyperlipidemia

Undesirable alterations in lipids have been observed with quetiapine use. Clinical monitoring, including baseline and periodic follow-up lipid evaluations in patients using quetiapine is recommended.

In some patients, a worsening of more than one of the metabolic parameters of weight, blood glucose and lipids was observed in clinical studies. Changes in these parameters should be managed as clinically appropriate.

Adults:

Table 3 shows the percentage of adult patients with changes in total cholesterol, triglycerides, LDL-cholesterol and HDL-cholesterol from baseline by indication in clinical trials with SEROQUEL.

Table 3: Percentage of Adult Patients with Shifts in Total Cholesterol, Triglycerides, LDL-Cholesterol and HDL-Cholesterol from Baseline to Clinically Significant Levels by Indication
Laboratory Analyte | Indication | Treatment Arm | N | Patients n (%)
Total Cholesterol; ≥ 240 mg/dL | Schizophrenia [6 weeks duration] | SEROQUEL | 137 | 24 (18%)
Total Cholesterol; ≥ 240 mg/dL | Schizophrenia [6 weeks duration] | Placebo | 92 | 6 (7%)
Total Cholesterol; ≥ 240 mg/dL | Bipolar Depression [8 weeks duration] | SEROQUEL | 463 | 41 (9%)
Total Cholesterol; ≥ 240 mg/dL | Bipolar Depression [8 weeks duration] | Placebo | 250 | 15 (6%)
Triglycerides; ≥200 mg/dL | Schizophrenia | SEROQUEL | 120 | 26 (22%)
Triglycerides; ≥200 mg/dL | Schizophrenia | Placebo | 70 | 11 (16%)
Triglycerides; ≥200 mg/dL | Bipolar Depression | SEROQUEL | 436 | 59 (14%)
Triglycerides; ≥200 mg/dL | Bipolar Depression | Placebo | 232 | 20 (9%)
LDL-Cholesterol; ≥ 160 mg/dL | Schizophrenia | SEROQUEL | na [Parameters not measured in the SEROQUEL registration studies for schizophrenia. Lipid parameters also were not measured in the bipolar mania registration studies.] | na
LDL-Cholesterol; ≥ 160 mg/dL | Schizophrenia | Placebo | na | na
LDL-Cholesterol; ≥ 160 mg/dL | Bipolar Depression | SEROQUEL | 465 | 29 (6%)
LDL-Cholesterol; ≥ 160 mg/dL | Bipolar Depression | Placebo | 256 | 12 (5%)
HDL-Cholesterol; ≤ 40 mg/dL | Schizophrenia | SEROQUEL | na | na
HDL-Cholesterol; ≤ 40 mg/dL | Schizophrenia | Placebo | na | na
HDL-Cholesterol; ≤ 40 mg/dL | Bipolar Depression | SEROQUEL | 393 | 56 (14%)
HDL-Cholesterol; ≤ 40 mg/dL | Bipolar Depression | Placebo | 214 | 29 (14%)

Children and Adolescents: Table 4 shows the percentage of children and adolescents with changes in total cholesterol, triglycerides, LDL-cholesterol and HDL-cholesterol from baseline in clinical trials with SEROQUEL.

Table 4: Percentage of Children and Adolescents with Shifts in Total Cholesterol, Triglycerides, LDL-Cholesterol and HDL-Cholesterol from Baseline to Clinically Significant Levels
Laboratory Analyte | Indication | Treatment Arm | N | Patients n (%)
Total Cholesterol; ≥ 200 mg/dL | Schizophrenia [13-17 years, 6 weeks duration] | SEROQUEL | 107 | 13 (12%)
Total Cholesterol; ≥ 200 mg/dL | Schizophrenia [13-17 years, 6 weeks duration] | Placebo | 56 | 1 (2%)
Total Cholesterol; ≥ 200 mg/dL | Bipolar Mania [10-17 years, 3 weeks duration] | SEROQUEL | 159 | 16 (10%)
Total Cholesterol; ≥ 200 mg/dL | Bipolar Mania [10-17 years, 3 weeks duration] | Placebo | 66 | 2 (3%)
Triglycerides; ≥150 mg/dL | Schizophrenia | SEROQUEL | 103 | 17 (17%)
Triglycerides; ≥150 mg/dL | Schizophrenia | Placebo | 51 | 4 (8%)
Triglycerides; ≥150 mg/dL | Bipolar Mania | SEROQUEL | 149 | 32 (22%)
Triglycerides; ≥150 mg/dL | Bipolar Mania | Placebo | 60 | 8 (13%)
LDL-Cholesterol; ≥ 130 mg/dL | Schizophrenia | SEROQUEL | 112 | 4 (4%)
LDL-Cholesterol; ≥ 130 mg/dL | Schizophrenia | Placebo | 60 | 1 (2%)
LDL-Cholesterol; ≥ 130 mg/dL | Bipolar Mania | SEROQUEL | 169 | 13 (8%)
LDL-Cholesterol; ≥ 130 mg/dL | Bipolar Mania | Placebo | 74 | 4 (5%)
HDL-Cholesterol; ≤ 40 mg/dL | Schizophrenia | SEROQUEL | 104 | 16 (15%)
HDL-Cholesterol; ≤ 40 mg/dL | Schizophrenia | Placebo | 54 | 10 (19%)
HDL-Cholesterol; ≤ 40 mg/dL | Bipolar Mania | SEROQUEL | 154 | 16 (10%)
HDL-Cholesterol; ≤ 40 mg/dL | Bipolar Mania | Placebo | 61 | 4 (7%)

5.6 Weight Gain

Increases in weight have been observed in clinical trials. Patients receiving quetiapine should receive regular monitoring of weight [see Patient Counseling Information (17)].

In some patients, a worsening of more than one of the metabolic parameters of weight, blood glucose and lipids was observed in clinical studies. Changes in these parameters should be managed as clinically appropriate.

Adults: In clinical trials with SEROQUEL the following increases in weight have been reported.

Table 5: Proportion of Patients with Weight Gain ≥7% of Body Weight (Adults)
Vital Sign | Indication | Treatment Arm | N | Patients n (%)
Weight Gain ≥7% of Body Weight | Schizophrenia | SEROQUEL | 391 | 89 (23%)
Weight Gain ≥7% of Body Weight | Schizophrenia | Placebo | 206 | 11 (6%)
Weight Gain ≥7% of Body Weight | Bipolar Mania (monotherapy) | SEROQUEL | 209 | 44 (21%)
Weight Gain ≥7% of Body Weight | Bipolar Mania (monotherapy) | Placebo | 198 | 13 (7%)
Weight Gain ≥7% of Body Weight | Bipolar Mania (adjunct therapy) | SEROQUEL | 196 | 25 (13%)
Weight Gain ≥7% of Body Weight | Bipolar Mania (adjunct therapy) | Placebo | 203 | 8 (4%)
Weight Gain ≥7% of Body Weight | Bipolar Depression | SEROQUEL | 554 | 47 (8%)
Weight Gain ≥7% of Body Weight | Bipolar Depression | Placebo | 295 | 7 (2%)

Children and Adolescents: In two clinical trials with SEROQUEL, one in bipolar mania and one in schizophrenia, reported increases in weight are included in the table below.

Table 6: Proportion of Patients with Weight Gain ≥7% of Body Weight (Children and Adolescents)
Vital Sign | Indication | Treatment Arm | N | Patients n (%)
Weight Gain ≥7% of Body Weight | Schizophrenia | SEROQUEL | 111 | 23 (21%)
Weight Gain ≥7% of Body Weight | Schizophrenia | Placebo | 44 | 3 (7%)
Weight Gain ≥7% of Body Weight | Bipolar Mania | SEROQUEL | 157 | 18 (12%)
Weight Gain ≥7% of Body Weight | Bipolar Mania | Placebo | 68 | 0 (0%)

The mean change in body weight in the schizophrenia trial was 2.0 kg in the SEROQUEL group and -0.4 kg in the placebo group and in the bipolar mania trial it was 1.7 kg in the SEROQUEL group and 0.4 kg in the placebo group.

In an open-label study that enrolled patients from the above two pediatric trials, 63% of patients (241/380) completed 26 weeks of therapy with SEROQUEL. After 26 weeks of treatment, the mean increase in body weight was 4.4 kg. Forty-five percent of the patients gained ≥ 7% of their body weight, not adjusted for normal growth. In order to adjust for normal growth over 26 weeks an increase of at least 0.5 standard deviation from baseline in BMI was used as a measure of a clinically significant change; 18.3% of patients on SEROQUEL met this criterion after 26 weeks of treatment.

When treating pediatric patients with SEROQUEL for any indication, weight gain should be assessed against that expected for normal growth.

5.7 Tardive Dyskinesia

A syndrome of potentially irreversible, involuntary, dyskinetic movements may develop in patients treated with antipsychotic drugs, including quetiapine. Although the prevalence of the syndrome appears to be highest among the elderly, especially elderly women, it is impossible to rely upon prevalence estimates to predict, at the inception of antipsychotic treatment, which patients are likely to develop the syndrome. Whether antipsychotic drug products differ in their potential to cause tardive dyskinesia is unknown.

The risk of developing tardive dyskinesia and the likelihood that it will become irreversible are believed to increase as the duration of treatment and the total cumulative dose of antipsychotic drugs administered to the patient increase. However, the syndrome can develop, although much less commonly, after relatively brief treatment periods at low doses or may even arise after discontinuation of treatment.

There is no known treatment for established cases of tardive dyskinesia, although the syndrome may remit, partially or completely, if antipsychotic treatment is withdrawn. Antipsychotic treatment, itself, however, may suppress (or partially suppress) the signs and symptoms of the syndrome and thereby may possibly mask the underlying process. The effect that symptomatic suppression has upon the long-term course of the syndrome is unknown.

Given these considerations, SEROQUEL should be prescribed in a manner that is most likely to minimize the occurrence of tardive dyskinesia. Chronic antipsychotic treatment should generally be reserved for patients who appear to suffer from a chronic illness that (1) is known to respond to antipsychotic drugs, and (2) for whom alternative, equally effective, but potentially less harmful treatments are not available or appropriate. In patients who do require chronic treatment, the smallest dose and the shortest duration of treatment producing a satisfactory clinical response should be sought. The need for continued treatment should be reassessed periodically.

If signs and symptoms of tardive dyskinesia appear in a patient on SEROQUEL, drug discontinuation should be considered. However, some patients may require treatment with SEROQUEL despite the presence of the syndrome.

5.8 Orthostatic Hypotension

Quetiapine may induce orthostatic hypotension associated with dizziness, tachycardia and, in some patients, syncope, especially during the initial dose-titration period, probably reflecting its α1-adrenergic antagonist properties. Syncope was reported in 1% (28/3265) of the patients treated with SEROQUEL, compared with 0.2% (2/954) on placebo and about 0.4% (2/527) on active control drugs. Orthostatic hypotension, dizziness, and syncope may lead to falls.

SEROQUEL should be used with particular caution in patients with known cardiovascular disease (history of myocardial infarction or ischemic heart disease, heart failure or conduction abnormalities), cerebrovascular disease or conditions which would predispose patients to hypotension (dehydration, hypovolemia and treatment with antihypertensive medications) [see Adverse Reactions (6.2)]. The risk of orthostatic hypotension and syncope may be minimized by limiting the initial dose to 25 mg twice daily [see Dosage and Administration (2)]. If hypotension occurs during titration to the target dose, a return to the previous dose in the titration schedule is appropriate.

5.9 Increases in Blood Pressure in Children and Adolescents

In placebo-controlled trials in children and adolescents with schizophrenia (6-week duration) or bipolar mania (3-week duration), the incidence of increases at any time in systolic blood pressure (≥20 mmHg) was 15.2% (51/335) for SEROQUEL and 5.5% (9/163) for placebo; the incidence of increases at any time in diastolic blood pressure (≥10 mmHg) was 40.6% (136/335) for SEROQUEL and 24.5% (40/163) for placebo. In the 26-week open-label clinical trial, one child with a reported history of hypertension experienced a hypertensive crisis. Blood pressure in children and adolescents should be measured at the beginning of, and periodically during treatment.

5.10 Leukopenia, Neutropenia and Agranulocytosis

In clinical trial and postmarketing experience, events of leukopenia/neutropenia have been reported temporally related to atypical antipsychotic agents, including SEROQUEL. Agranulocytosis (including fatal cases) has also been reported.

Possible risk factors for leukopenia/neutropenia include pre-existing low white cell count (WBC) and history of drug induced leukopenia/neutropenia. Patients with a pre-existing low WBC or a history of drug induced leukopenia/neutropenia should have their complete blood count (CBC) monitored frequently during the first few months of therapy and should discontinue SEROQUEL at the first sign of a decline in WBC in absence of other causative factors.

Patients with neutropenia should be carefully monitored for fever or other symptoms or signs of infection and treated promptly if such symptoms or signs occur. Patients with severe neutropenia (absolute neutrophil count <1000/mm^3) should discontinue SEROQUEL and have their WBC followed until recovery [see Adverse Reactions (6.2)].

5.11 Cataracts

The development of cataracts was observed in association with quetiapine treatment in chronic dog studies [see Nonclinical Toxicology, Animal Toxicology (13.2)]. Lens changes have also been observed in adults, children and adolescents during long-term SEROQUEL treatment, but a causal relationship to SEROQUEL use has not been established. Nevertheless, the possibility of lenticular changes cannot be excluded at this time. Therefore, examination of the lens by methods adequate to detect cataract formation, such as slit lamp exam or other appropriately sensitive methods, is recommended at initiation of treatment or shortly thereafter, and at 6-month intervals during chronic treatment.

5.12 QT Prolongation

In clinical trials quetiapine was not associated with a persistent increase in QT intervals. However, the QT effect was not systematically evaluated in a thorough QT study. In post marketing experience, there were cases reported of QT prolongation in patients who overdosed on quetiapine [see Overdosage (10.1)], in patients with concomitant illness, and in patients taking medicines known to cause electrolyte imbalance or increase QT interval [see Drug Interactions (7)].

The use of quetiapine should be avoided in combination with other drugs that are known to prolong QTc including Class 1A antiarrythmics (e.g., quinidine, procainamide) or Class III antiarrythmics (e.g., amiodarone, sotalol), antipsychotic medications (e.g., ziprasidone, chlorpromazine, thioridazine), antibiotics (e.g., gatifloxacin, moxifloxacin), or any other class of medications known to prolong the QTc interval (e.g., pentamidine, levomethadyl acetate, methadone).

Quetiapine should also be avoided in circumstances that may increase the risk of occurrence of torsade de pointes and/or sudden death including (1) a history of cardiac arrhythmias such as bradycardia; (2) hypokalemia or hypomagnesemia; (3) concomitant use of other drugs that prolong the QTc interval; and (4) presence of congenital prolongation of the QT interval.

Caution should also be exercised when quetiapine is prescribed in patients with increased risk of QT prolongation (e.g. cardiovascular disease, family history of QT prolongation, the elderly, congestive heart failure and heart hypertrophy).

5.13 Seizures

During clinical trials, seizures occurred in 0.5% (20/3490) of patients treated with SEROQUEL compared to 0.2% (2/954) on placebo and 0.7% (4/527) on active control drugs. As with other antipsychotics, SEROQUEL should be used cautiously in patients with a history of seizures or with conditions that potentially lower the seizure threshold, e.g., Alzheimer’s dementia. Conditions that lower the seizure threshold may be more prevalent in a population of 65 years or older.

5.14 Hypothyroidism

Adults: Clinical trials with quetiapine demonstrated dose-related decreases in thyroid hormone levels. The reduction in total and free thyroxine (T4) of approximately 20% at the higher end of the therapeutic dose range was maximal in the first six weeks of treatment and maintained without adaptation or progression during more chronic therapy. In nearly all cases, cessation of quetiapine treatment was associated with a reversal of the effects on total and free T4, irrespective of the duration of treatment. About 0.7% (26/3489) of SEROQUEL patients did experience TSH increases in monotherapy studies. Some patients with TSH increases needed replacement thyroid treatment. In the mania adjunct studies, where SEROQUEL was added to lithium or divalproex, 12% (24/196) of SEROQUEL treated patients compared to 7% (15/203) of placebo-treated patients had elevated TSH levels. Of the SEROQUEL treated patients with elevated TSH levels, 3 had simultaneous low free T4 levels.

In all quetiapine trials, the incidence of potentially clinically significant shifts in thyroid hormones and TSH were*: decrease in free T4, 2.0% (357/17513); decrease in total T4, 4.0% (75/1861); decrease in free T3, 0.4% (53/13766); decrease in total T3, 2.0% (26/1312), and increase in TSH, 4.9% (956/19412). In eight patients, where TBG was measured, levels of TBG were unchanged.

Table 7 shows the incidence of these shifts in short-term placebo-controlled clinical trials.

Table 7: Incidence of potentially clinically significant shifts in thyroid hormone levels and TSH in short term placebo-controlled clinical trials
Total T4 |  | Free T4 |  | Total T3 |  | Free T3 |  | TSH
Quetiapine | Placebo | Quetiapine | Placebo | Quetiapine | Placebo | Quetiapine | Placebo | Quetiapine | Placebo
3.4 %; (37/1097) | 0.6%; (4/651) | 0.7%; (52/7218) | 0.1%; (4/3668) | 0.5%; (2/369) | 0.0%; (0/113) | 0.2%; (11/5673) | 0.0%; (1/2679) | 3.2%; (240/7587) | 2.7%; (105/3912)

In short-term placebo-controlled monotherapy trials, the incidence of reciprocal, potentially clinically significant shifts in T3 and TSH was 0.0 % for both quetiapine (1/4800) and placebo (0/2190) and for T4 and TSH the shifts were 0.1% (7/6154) for quetiapine versus 0.0% (1/3007) for placebo.

Generally, these changes in thyroid hormone levels were of no clinical significance.

Children and Adolescents: In acute placebo-controlled trials in children and adolescent patients with schizophrenia (6-week duration) or bipolar mania (3-week duration), the incidence of shifts to potentially clinically important thyroid function values at any time for SEROQUEL treated patients and placebo-treated patients for elevated TSH was 2.9% (8/280) vs. 0.7% (1/138), respectively and for decreased total thyroxine was 2.8% (8/289) vs. 0% (0/145, respectively). Of the SEROQUEL treated patients with elevated TSH levels, 1 had simultaneous low free T4 level at end of treatment.

5.15 Hyperprolactinemia

Adults: During clinical trials with quetiapine, the incidence of shifts in prolactin levels to a clinically significant value occurred in 3.6% (158/4416) of patients treated with quetiapine compared to 2.6% (51/1968) on placebo.

Children and Adolescents: In acute placebo-controlled trials in children and adolescent patients with bipolar mania (3-week duration) or schizophrenia (6-week duration), the incidence of shifts in prolactin levels to a clinically significant value (>20 µg/L males; > 26 µg/L females at any time) was 13.4% (18/134) for SEROQUEL compared to 4% (3/75) for placebo in males and 8.7% (9/104) for SEROQUEL compared to 0% (0/39) for placebo in females.

Like other drugs that antagonize dopamine D2 receptors, SEROQUEL elevates prolactin levels in some patients and the elevation may persist during chronic administration. Hyperprolactinemia, regardless of etiology, may suppress hypothalamic GnRH, resulting in reduced pituitary gonadotrophin secretion. This, in turn, may inhibit reproductive function by impairing gonadal steroidogenesis in both female and male patients. Galactorrhea, amenorrhea, gynecomastia, and impotence have been reported in patients receiving prolactin-elevating compounds. Long-standing hyperprolactinemia when associated with hypogonadism may lead to decreased bone density in both female and male subjects.

Tissue culture experiments indicate that approximately one-third of human breast cancers are prolactin dependent in vitro, a factor of potential importance if the prescription of these drugs is considered in a patient with previously detected breast cancer. As is common with compounds which increase prolactin release, mammary gland, and pancreatic islet cell neoplasia (mammary adenocarcinomas, pituitary and pancreatic adenomas) was observed in carcinogenicity studies conducted in mice and rats. Neither clinical studies nor epidemiologic studies conducted to date have shown an association between chronic administration of this class of drugs and tumorigenesis in humans, but the available evidence is too limited to be conclusive [see Carcinogenesis, Mutagenesis, Impairment of Fertility (13.1)].

5.16 Transaminase Elevations

Asymptomatic, transient and reversible elevations in serum transaminases (primarily ALT) have been reported. In schizophrenia trials in adults, the proportions of patients with transaminase elevations of > 3 times the upper limits of the normal reference range in a pool of 3- to 6-week placebo-controlled trials were approximately 6% (29/483) for SEROQUEL compared to 1% (3/194) for placebo. In acute bipolar mania trials in adults, the proportions of patients with transaminase elevations of > 3 times the upper limits of the normal reference range in a pool of 3- to 12-week placebo-controlled trials were approximately 1% for both SEROQUEL (3/560) and placebo (3/294). These hepatic enzyme elevations usually occurred within the first 3 weeks of drug treatment and promptly returned to pre-study levels with ongoing treatment with SEROQUEL. In bipolar depression trials, the proportions of patients with transaminase elevations of > 3 times the upper limits of the normal reference range in two 8-week placebo-controlled trials was 1% (5/698) for SEROQUEL and 2% (6/347) for placebo.

5.17 Potential for Cognitive and Motor Impairment

Somnolence was a commonly reported adverse event reported in patients treated with SEROQUEL especially during the 3-5 day period of initial dose-titration. In schizophrenia trials, somnolence was reported in 18% (89/510) of patients on SEROQUEL compared to 11% (22/206) of placebo patients. In acute bipolar mania trials using SEROQUEL as monotherapy, somnolence was reported in 16% (34/209) of patients on SEROQUEL compared to 4% of placebo patients. In acute bipolar mania trials using SEROQUEL as adjunct therapy, somnolence was reported in 34% (66/196) of patients on SEROQUEL compared to 9% (19/203) of placebo patients. In bipolar depression trials, somnolence was reported in 57% (398/698) of patients on SEROQUEL compared to 15% (51/347) of placebo patients. Since SEROQUEL has the potential to impair judgment, thinking, or motor skills, patients should be cautioned about performing activities requiring mental alertness, such as operating a motor vehicle (including automobiles) or operating hazardous machinery until they are reasonably certain that SEROQUEL therapy does not affect them adversely. Somnolence may lead to falls.

5.18 Priapism

One case of priapism in a patient receiving SEROQUEL has been reported prior to market introduction. While a causal relationship to use of SEROQUEL has not been established, other drugs with alpha-adrenergic blocking effects have been reported to induce priapism, and it is possible that SEROQUEL may share this capacity. Severe priapism may require surgical intervention.

5.19 Body Temperature Regulation

Although not reported with SEROQUEL, disruption of the body's ability to reduce core body temperature has been attributed to antipsychotic agents. Appropriate care is advised when prescribing SEROQUEL for patients who will be experiencing conditions which may contribute to an elevation in core body temperature, e.g., exercising strenuously, exposure to extreme heat, receiving concomitant medication with anticholinergic activity, or being subject to dehydration.

5.20 Dysphagia

Esophageal dysmotility and aspiration have been associated with antipsychotic drug use. Aspiration pneumonia is a common cause of morbidity and mortality in elderly patients, in particular those with advanced Alzheimer's dementia. SEROQUEL and other antipsychotic drugs should be used cautiously in patients at risk for aspiration pneumonia.

5.21 Suicide

The possibility of a suicide attempt is inherent in bipolar disorder and schizophrenia; close supervision of high risk patients should accompany drug therapy. Prescriptions for SEROQUEL should be written for the smallest quantity of tablets consistent with good patient management in order to reduce the risk of overdose.

In two 8-week clinical studies in patients with bipolar depression (N=1048), the incidence of treatment emergent suicidal ideation or suicide attempt was low and similar to placebo (SEROQUEL 300 mg, 6/350, 1.7%; SEROQUEL 600 mg, 9/348, 2.6%; Placebo, 7/347, 2.0%).

5.22 Use in Patients with Concomitant Illness

Clinical experience with SEROQUEL in patients with certain concomitant systemic illnesses is limited [see Pharmacokinetics (12.3)].

SEROQUEL has not been evaluated or used to any appreciable extent in patients with a recent history of myocardial infarction or unstable heart disease. Patients with these diagnoses were excluded from premarketing clinical studies. Because of the risk of orthostatic hypotension with SEROQUEL, caution should be observed in cardiac patients [see Warnings and Precautions (5.8)].

5.23 Withdrawal

Acute withdrawal symptoms, such as insomnia, nausea, and vomiting have been described after abrupt cessation of atypical antipsychotic drugs, including SEROQUEL. In short-term placebo-controlled, monotherapy clinical trials with SEROQUEL XR that included a discontinuation phase which evaluated discontinuation symptoms, the aggregated incidence of patients experiencing one or more discontinuation symptoms after abrupt cessation was 12.1% (241/1993) for SEROQUEL XR and 6.7% (71/1065) for placebo. The incidence of the individual adverse events (i.e., insomnia, nausea, headache, diarrhea, vomiting, dizziness and irritability) did not exceed 5.3% in any treatment group and usually resolved after 1 week post-discontinuation. Gradual withdrawal is advised.

6 ADVERSE REACTIONS

6.1 Clinical Study Experience

Adults

Because clinical studies are conducted under widely varying conditions, adverse reaction rates observed in the clinical studies of a drug cannot be directly compared to rates in the clinical studies of another drug and may not reflect the rates observed in practice.

The information below is derived from a clinical trial database for SEROQUEL consisting of over 4300 patients. This database includes 698 patients exposed to SEROQUEL for the treatment of bipolar depression, 405 patients exposed to SEROQUEL for the treatment of acute bipolar mania (monotherapy and adjunct therapy), 646 patients exposed to SEROQUEL for the maintenance treatment of bipolar I disorder as adjunct therapy, and approximately 2600 patients and/or normal subjects exposed to 1 or more doses of SEROQUEL for the treatment of schizophrenia.

Of these approximately 4300 subjects, approximately 4000 (2300 in schizophrenia, 405 in acute bipolar mania, 698 in bipolar depression, and 646 for the maintenance treatment of bipolar I disorder) were patients who participated in multiple dose effectiveness trials, and their experience corresponded to approximately 2400 patient-years. The conditions and duration of treatment with SEROQUEL varied greatly and included (in overlapping categories) open-label and double-blind phases of studies, inpatients and outpatients, fixed-dose and dose-titration studies, and short-term or longer-term exposure. Adverse reactions were assessed by collecting adverse events, results of physical examinations, vital signs, weights, laboratory analyses, ECGs, and results of ophthalmologic examinations.

Adverse reactions during exposure were obtained by general inquiry and recorded by clinical investigators using terminology of their own choosing. Consequently, it is not possible to provide a meaningful estimate of the proportion of individuals experiencing adverse reactions without first grouping similar types of reactions into a smaller number of standardized reaction categories.

In the tables and tabulations that follow, standard COSTART terminology has been used to classify reported adverse reactions for schizophrenia and bipolar mania. MedDRA terminology has been used to classify reported adverse reactions for bipolar depression.

The stated frequencies of adverse reactions represent the proportion of individuals who experienced, at least once, a treatment-emergent adverse reaction of the type listed. A reaction was considered treatment emergent if it occurred for the first time or worsened while receiving therapy following baseline evaluation.

Incidence of Adverse Reactions in Short-Term, Placebo-Controlled Trials in Adults

Adverse Reactions Associated with Discontinuation of Treatment in Short-Term, Placebo-Controlled Trials:

Schizophrenia: Overall, there was little difference in the incidence of discontinuation due to adverse reactions (4% for SEROQUEL vs. 3% for placebo) in a pool of controlled trials. However, discontinuations due to somnolence (0.8% SEROQUEL vs. 0% placebo) and hypotension (0.4% SEROQUEL vs. 0% placebo) were considered to be drug related [see Warnings and Precautions (5.8 and 5.17)].

Bipolar Disorder:

Mania: Overall, discontinuations due to adverse reactions were 5.7% for SEROQUEL vs. 5.1% for placebo in monotherapy and 3.6% for SEROQUEL vs. 5.9% for placebo in adjunct therapy.

Depression: Overall, discontinuations due to adverse reactions were 12.3% for SEROQUEL 300 mg vs. 19.0% for SEROQUEL 600 mg and 5.2% for placebo.

Commonly Observed Adverse Reactions in Short-Term, Placebo-Controlled Trials:

In the acute therapy of schizophrenia (up to 6 weeks) and bipolar mania (up to 12 weeks) trials, the most commonly observed adverse reactions associated with the use of SEROQUEL monotherapy (incidence of 5% or greater) and observed at a rate on SEROQUEL at least twice that of placebo were somnolence (18%), dizziness (11%), dry mouth (9%), constipation (8%), ALT increased (5%), weight gain (5%), and dyspepsia (5%).

Adverse Reactions Occurring at an Incidence of 1% or More Among SEROQUEL Treated Patients in Short-Term, Placebo-Controlled Trials:

The prescriber should be aware that the figures in the tables and tabulations cannot be used to predict the incidence of side effects in the course of usual medical practice where patient characteristics and other factors differ from those that prevailed in the clinical trials. Similarly, the cited frequencies cannot be compared with figures obtained from other clinical investigations involving different treatments, uses, and investigators. The cited figures, however, do provide the prescribing physician with some basis for estimating the relative contribution of drug and nondrug factors to the side effect incidence in the population studied.

Table 8 enumerates the incidence, rounded to the nearest percent, of treatment-emergent adverse reactions that occurred during acute therapy of schizophrenia (up to 6 weeks) and bipolar mania (up to 12 weeks) in 1% or more of patients treated with SEROQUEL (doses ranging from 75 to 800 mg/day) where the incidence in patients treated with SEROQUEL was greater than the incidence in placebo-treated patients.

Table 8: Treatment-Emergent Adverse Reaction Incidence in 3- to 12-Week Placebo-Controlled Clinical Trials for the Treatment of Schizophrenia and Bipolar Mania (Monotherapy)
Body System/ Preferred Term | SEROQUEL (n=719) | PLACEBO (n=404)
Body as a Whole
Headache | 21% | 14%
Pain | 7% | 5%
Asthenia | 5% | 3%
Abdominal Pain | 4% | 1%
Back Pain | 3% | 1%
Fever | 2% | 1%
Cardiovascular
Tachycardia | 6% | 4%
Postural Hypotension | 4% | 1%
Digestive
Dry Mouth | 9% | 3%
Constipation | 8% | 3%
Vomiting | 6% | 5%
Dyspepsia | 5% | 1%
Gastroenteritis | 2% | 0%
Gamma Glutamyl Transpeptidase Increased | 1% | 0%
Metabolic and Nutritional
Weight Gain | 5% | 1%
ALT Increased | 5% | 1%
AST Increased | 3% | 1%
Nervous
Agitation | 20% | 17%
Somnolence | 18% | 8%
Dizziness | 11% | 5%
Anxiety | 4% | 3%
Respiratory
Pharyngitis | 4% | 3%
Rhinitis | 3% | 1%
Skin and Appendages
Rash | 4% | 2%
Special Senses
Amblyopia | 2% | 1%

In the acute adjunct therapy of bipolar mania (up to 3 weeks) studies, the most commonly observed adverse reactions associated with the use of SEROQUEL (incidence of 5% or greater) and observed at a rate on SEROQUEL at least twice that of placebo were somnolence (34%), dry mouth (19%), asthenia (10%), constipation (10%), abdominal pain (7%), postural hypotension (7%), pharyngitis (6%), and weight gain (6%).

Table 9 enumerates the incidence, rounded to the nearest percent, of treatment-emergent adverse reactions that occurred during therapy (up to 3 weeks) of acute mania in 1% or more of patients treated with SEROQUEL (doses ranging from 100 to 800 mg/day) used as adjunct therapy to lithium and divalproex where the incidence in patients treated with SEROQUEL was greater than the incidence in placebo-treated patients.

Table 9: Treatment-Emergent Adverse Reaction Incidence in 3-Week Placebo-Controlled Clinical Trials for the Treatment of Bipolar Mania (Adjunct Therapy)
Body System/ Preferred Term | SEROQUEL (n=196) | PLACEBO (n=203)
Body as a Whole
Headache | 17% | 13%
Asthenia | 10% | 4%
Abdominal Pain | 7% | 3%
Back Pain | 5% | 3%
Hormone Level Altered | 3% | 0%
Heaviness | 2% | 1%
Infection | 2% | 1%
Fever | 2% | 1%
Neck Rigidity | 1% | 0%
Cardiovascular
Postural Hypotension | 7% | 2%
Hypotension | 3% | 1%
Hypertension | 2% | 1%
Tachycardia | 2% | 1%
Hemorrhage | 1% | 0%
Digestive
Dry Mouth | 19% | 3%
Constipation | 10% | 5%
Dyspepsia | 4% | 3%
Increased Appetite | 2% | 1%
Flatulence | 1% | 0%
Gastrointestinal Disorder | 1% | 0%
Endocrine
Hypothyroidism | 2% | 1%
Hemic and Lymphatic
Lymphadenopathy | 1% | 0%
Metabolic and Nutritional
Weight Gain | 6% | 3%
Peripheral Edema | 4% | 2%
Musculoskeletal
Twitching | 4% | 1%
Joint Disorder | 1% | 0%
Nervous
Somnolence | 34% | 9%
Dizziness | 9% | 6%
Tremor | 8% | 7%
Agitation | 6% | 4%
Hypertonia | 4% | 3%
Depression | 3% | 2%
Speech Disorder | 3% | 1%
Incoordination | 2% | 1%
Thinking Abnormal | 2% | 0%
Anxiety | 2% | 0%
Ataxia | 2% | 0%
Respiratory
Pharyngitis | 6% | 3%
Rhinitis | 4% | 2%
Sinusitis | 2% | 1%
Skin and Appendages
Sweating | 2% | 1%
Special Senses
Amblyopia | 3% | 2%
Ear Disorder | 1% | 0%
Ear Pain | 1% | 0%
Urogenital
Urinary Tract Infection | 2% | 1%
Female Lactation | 1% | 0%
Impotence | 1% | 0%
Urinary Tract Disorder | 1% | 0%

In bipolar depression studies (up to 8 weeks), the most commonly observed treatment emergent adverse reactions associated with the use of SEROQUEL (incidence of 5% or greater) and observed at a rate on SEROQUEL at least twice that of placebo were somnolence (57%), dry mouth (44%), dizziness (18%), constipation (10%), and lethargy (5%).

Table 10 enumerates the incidence, rounded to the nearest percent, of treatment-emergent adverse reactions that occurred during therapy (up to 8 weeks) of bipolar depression in 1% or more of patients treated with SEROQUEL (doses of 300 and 600 mg/day) where the incidence in patients treated with SEROQUEL was greater than the incidence in placebo-treated patients.

Table 10: Treatment-Emergent Adverse Reaction Incidence in 8-Week Placebo-Controlled Clinical Trials for the Treatment of Bipolar Depression
Body System / Preferred Term | SEROQUEL (n=698) | PLACEBO (n=347)
Cardiac Disorders
Palpitations | 4% | 1%
Tachycardia | 1% | 0%
Eye Disorders
Vision Blurred | 4% | 2%
Gastrointestinal Disorders
Dry Mouth | 44% | 13%
Constipation | 10% | 4%
Dyspepsia | 7% | 4%
Vomiting | 5% | 4%
Gastroesophageal Reflux Disease | 2% | 1%
Dysphagia | 2% | 0%
General Disorders and Administrative Site Conditions
Fatigue | 10% | 8%
Asthenia | 2% | 1%
Injury, Poisoning and Procedural Complications
Injury | 1% | 0%
Investigations
Weight increased | 4% | 1%
Metabolism and Nutrition Disorders
Increased Appetite | 5% | 3%
Musculoskeletal and Connective Tissue Disorders
Arthralgia | 3% | 2%
Pain in Extremity | 2% | 1%
Nervous System Disorders
Somnolence | 57% | 15%
Dizziness | 18% | 7%
Lethargy | 5% | 2%
Akathisia | 4% | 1%
Extrapyramidal Disorder | 3% | 1%
Paraesthesia | 3% | 2%
Dysarthria | 3% | 0%
Hypersomnia | 3% | 0%
Tremor | 2% | 1%
Restless Legs Syndrome | 2% | 0%
Balance Disorder | 2% | 1%
Hypoaesthesia | 2% | 1%
Dystonia | 1% | 0%
Dizziness, postural | 1% | 0%
Dyskinesia | 1% | 0%
Dysgeusia | 1% | 0%
Psychiatric disorders
Irritability | 3% | 1%
Abnormal Dreams | 2% | 1%
Confusional State | 1% | 0%
Respiratory, Thoracic, and Mediastinal Disorders
Nasal Congestion | 5% | 3%
Cough | 3% | 1%
Sinus Congestion | 2% | 1%
Vascular Disorders
Orthostatic Hypotension | 4% | 3%
Hypertension | 1% | 0%

Explorations for interactions on the basis of gender, age, and race did not reveal any clinically meaningful differences in the adverse reaction occurrence on the basis of these demographic factors.

Dose Dependency of Adverse Reactions in Short-Term, Placebo-Controlled Trials

Dose-related Adverse Reactions: Spontaneously elicited adverse reaction data from a study of schizophrenia comparing five fixed doses of SEROQUEL (75 mg, 150 mg, 300 mg, 600 mg, and 750 mg/day) to placebo were explored for dose-relatedness of adverse reactions. Logistic regression analyses revealed a positive dose response (p<0.05) for the following adverse reactions: dyspepsia, abdominal pain, and weight gain.

Adverse Reactions in clinical trials with quetiapine and not listed elsewhere in the label:

The following adverse reactions have also been reported with quetiapine: nightmares, hypersensitivity and elevations in serum creatine phosphokinase (not associated with NMS).

Extrapyramidal Symptoms:

Dystonia

Class Effect: Symptoms of dystonia, prolonged abnormal contractions of muscle groups, may occur in susceptible individuals during the first few days of treatment. Dystonic symptoms include: spasm of the neck muscles, sometimes progressing to tightness of the throat, swallowing difficulty, difficulty breathing, and/or protrusion of the tongue. While these symptoms can occur at low doses, they occur more frequently and with greater severity with high potency and at higher doses of first generation antipsychotic drugs. An elevated risk of acute dystonia is observed in males and younger age groups.

Adults: Data from one 6-week clinical trial of schizophrenia comparing five fixed doses of SEROQUEL (75, 150, 300, 600, 750 mg/day) provided evidence for the lack of treatment-emergent extrapyramidal symptoms (EPS) and dose-relatedness for EPS associated with SEROQUEL treatment. Three methods were used to measure EPS: (1) Simpson-Angus total score (mean change from baseline) which evaluates Parkinsonism and akathisia, (2) incidence of spontaneous complaints of EPS (akathisia, akinesia, cogwheel rigidity, extrapyramidal syndrome, hypertonia, hypokinesia, neck rigidity, and tremor), and (3) use of anticholinergic medications to treat emergent EPS.

Table 11: Adverse experiences potentially associated with EPS in a short-term, placebo-controlled multiple fixed-dose Phase III schizophrenia trial (6 weeks duration)
Preferred Term | Placebo (N=51) |  | SEROQUEL 75 mg/day (N=53) |  | SEROQUEL 150 mg/day (N=48) |  | SEROQUEL 300 mg/day (N=52) |  | SEROQUEL 600 mg/day (N=51) |  | SEROQUEL 750 mg/day (N=54)
 | n | % | n | % | n | % | n | % | n | % | n | %
Dystonic event | 4 | 7.8 | 2 | 3.8 | 2 | 4.2 | 0 | 0.0 | 2 | 3.9 | 3 | 5.6
Parkinsonism | 4 | 7.8 | 2 | 3.8 | 0 | 0.0 | 1 | 1.9 | 1 | 2.0 | 1 | 1.9
Akathisia | 4 | 7.8 | 1 | 1.9 | 1 | 2.1 | 0 | 0.0 | 0 | 0.0 | 1 | 1.9
Dyskinetic event | 0 | 0.0 | 2 | 3.8 | 0 | 0.0 | 0 | 0.0 | 1 | 2.0 | 0 | 0.0
Other extraphyrmidal event | 4 | 7.8 | 2 | 3.8 | 0 | 0.0 | 3 | 5.8 | 3 | 5.9 | 1 | 1.9

Parkinsonism incidence rates as measured by the Simpson-Angus total score for placebo and the five fixed doses (75, 150, 300, 600, 750 mg/day) were: -0.6; -1.0, -1.2; -1.6; -1.8 and -1.8. The rate of anticholinergic medication use to treat emergent EPS for placebo and the five fixed doses was: 14%; 11%; 10%; 8%; 12% and 11%.

In six additional placebo-controlled clinical trials (3 in acute mania and 3 in schizophrenia) using variable doses of SEROQUEL, there were no differences between the SEROQUEL and placebo treatment groups in the incidence of EPS, as assessed by Simpson-Angus total scores, spontaneous complaints of EPS and the use of concomitant anticholinergic medications to treat EPS.

In two placebo-controlled clinical trials for the treatment of bipolar depression using 300 mg and 600 mg of SEROQUEL, the incidence of adverse reactions potentially related to EPS was 12% in both dose groups and 6% in the placebo group. In these studies, the incidence of the individual adverse reactions (akathisia, extrapyramidal disorder, tremor, dyskinesia, dystonia, restlessness, muscle contractions involuntary, psychomotor hyperactivity and muscle rigidity) were generally low and did not exceed 4% in any treatment group.

The 3 treatment groups were similar in mean change in SAS total score and BARS Global Assessment score at the end of treatment. The use of concomitant anticholinergic medications was infrequent and similar across the three treatment groups.

Children and Adolescents:

The information below is derived from a clinical trial database for SEROQUEL consisting of over 1000 pediatric patients. This database includes 677 patients exposed to SEROQUEL for the treatment of schizophrenia and 393 patients exposed to SEROQUEL for the treatment of acute bipolar mania.

Incidence of Adverse Reactions in Short-Term, Placebo-Controlled Trials in Children and Adolescents

Adolescents 13 to 17 years of age with Schizophrenia

The following findings were based on a 6-week placebo-controlled trial in which quetiapine was administered in either doses of 400 or 800 mg/day.

Adverse Reactions Associated with Discontinuation of Treatment

The incidence of discontinuation due to adverse reactions for quetiapine-treated and placebo-treated patients was 8.2% and 2.7%, respectively. The adverse event leading to discontinuation in 1% or more of patients on SEROQUEL and at a greater incidence than placebo was somnolence (2.7% and 0% for placebo).

Commonly Observed Adverse Reactions

In therapy for schizophrenia (up to 6 weeks), the most commonly observed adverse reactions associated with the use of quetiapine in adolescents (incidence of 5% or greater and quetiapine incidence at least twice that for placebo) were somnolence (34%), dizziness (12%), dry mouth (7%), tachycardia (7%).

Table 12 enumerates the incidence, rounded to the nearest percent, of treatment-emergent adverse reactions that occurred during therapy (up to 6 weeks) of schizophrenia in 5% or more of patients treated with SEROQUEL (doses of 400 or 800 mg/day) where the incidence in patients treated with SEROQUEL was at least twice the incidence in placebo-treated patients.

Adverse events that were potentially dose-related with higher frequency in the 800 mg group compared to the 400 mg group included dizziness (8.2% vs. 14.9%), dry mouth (4.1% vs. 9.5%), and tachycardia (5.5% vs. 8.1%).

Table 12: Treatment-Emergent Adverse Reaction Incidence in a 6-Week Placebo-Controlled Clinical Trial for the Treatment of Schizophrenia in Adolescent Patients
Body System/Preferred Term | SEROQUEL (n=147) | PLACEBO (n=75)
Central Nervous System Disorders
Somnolence | 34% | 11%
Digestive
Dry Mouth | 7% | 1%
Cardiovascular Disorders
Tachycardia | 7% | 0%
Nervous System Disorder
Dizziness | 12% | 5%

Children and Adolescents 10 to 17 years of age with Bipolar Mania

The following findings were based on a 3-week placebo-controlled trial in which quetiapine was administered in either doses of 400 or 600 mg/day.

Adverse Reactions Associated with Discontinuation of Treatment

The incidence of discontinuation due to adverse reactions for quetiapine-treated and placebo-treated patients was 11.4% and 4.4%, respectively. The adverse events leading to discontinuation in 1% or more of patients on SEROQUEL and at a greater incidence than placebo were somnolence (4.1% vs. 1.1%), fatigue (2.1% vs. 0), irritability (1.6% vs. 0) and syncope (1% vs. 0).

Commonly Observed Adverse Reactions

In bipolar mania therapy (up to 3 weeks) the most commonly observed adverse reactions associated with the use of quetiapine in children and adolescents (incidence of 5% or greater and quetiapine incidence at least twice that for placebo) were somnolence (53%), dizziness (18%), fatigue (11%), increased appetite (9%), nausea (8%), vomiting (8%), tachycardia (7%), dry mouth (7%), and weight increased (6%).

Table 13 enumerates the incidence, rounded to the nearest percent, of treatment-emergent adverse reactions that occurred during therapy (up to 3 weeks) of bipolar mania in 5% or more of patients treated with SEROQUEL (doses of 400 or 600 mg/day) where the incidence in patients treated with SEROQUEL was at least twice the incidence in placebo-treated patients.

Adverse events that were potentially dose-related with higher frequency in the 600 mg group compared to the 400 mg group included somnolence (49% vs. 57%), nausea (6.3% vs. 10.2%) and tachycardia (5.3% vs. 8.2%).

Table 13: Treatment-Emergent Adverse Reaction Incidence in a 3-Week Placebo-Controlled Clinical Trial for the Treatment of Bipolar Mania in Children and Adolescent Patients
Body System/Preferred Term | SEROQUEL (n=193) | PLACEBO (n=90)
Nervous System Disorders
Somnolence | 53% | 14%
Dizziness | 18% | 2%
Fatigue | 11% | 4%
Metabolism and Nutrition Disorders
Increased Appetite | 9% | 1%
Weight Increased | 6% | 0%
Gastrointestinal Disorders
Nausea | 8% | 4%
Vomiting | 8% | 3%
Dry Mouth | 7% | 0%
Cardiac Disorders
Tachycardia | 7% | 0%

Adverse Reactions in Schizophrenia and Bipolar Mania Clinical Trials

Commonly Observed Adverse Reactions

In acute therapy for schizophrenia and bipolar mania (up to 6 weeks in schizophrenia and up to 3 weeks in bipolar mania) the most commonly observed adverse reactions associated with the use of quetiapine in children and adolescents (incidence of 5% or greater and quetiapine incidence at least twice that for placebo) were somnolence (47%), dizziness (15%), fatigue (9%), increased appetite (8%), dry mouth (7%), tachycardia (7%), and weight increased (5%).

Table 14 enumerates the pooled incidence of adverse reactions that occurred during acute therapy of children and adolescents (up to 6 weeks in schizophrenia and up to 3 weeks in bipolar mania). The table includes only those reactions that occurred in 1% or more of patients treated with quetiapine (doses of 400, 600, or 800 mg/day) and for which the incidence in patients treated with quetiapine was greater than the incidence in patients treated with placebo.

Table 14: Adverse Reactions (incidence ≥ 1% and greater than placebo) in Short-Term, Placebo-Controlled Trials of Children and Adolescents (10 to 17 years of age) with Bipolar Mania or Schizophrenia
Body System/Preferred Term | SEROQUEL (n=340) | PLACEBO (n=165)
Central/Nervous System Disorder
Somnolence | 47% | 15%
Dizziness | 15% | 4%
Fatigue | 9% | 4%
Irritability | 4% | 1%
Tremor | 3% | 2%
Akathisia | 2% | 1%
Syncope | 2% | 0%
Lethargy | 1% | 0%
Metabolism and Nutrition Disorders
Increased Appetite | 8% | 2%
Weight Increased | 5% | 1%
Digestive
Dry Mouth | 7% | 1%
Cardiovascular Disorders
Tachycardia | 8% | 0%
Musculoskeletal and Connective Tissue Disorders
Arthralgia | 3% | 1%
Back Pain | 2% | 1%
Musculoskeletal Stiffness | 2% | 1%
Respiratory, Thoracic and Mediastinal Disorder
Nasal Congestion | 3% | 2%
Gastrointestinal Disorder
Vomiting | 7% | 6%
Stomach Discomfort | 2% | 1%
Skin and Subcutaneous Tissue Disorders
Acne | 2% | 1%
General Disorders and Administration Site Conditions
Pyrexia | 2% | 1%
Asthenia | 2% | 1%
Psychiatric Disorders
Aggression | 2% | 1%
Restlessness | 1% | 0%
Eye Disorders
Vision Blurred | 2% | 1%
Infections and Infestations
Tooth Abscess | 1% | 0%

Extrapyramidal Symptoms:

In a short-term placebo-controlled monotherapy trial in adolescent patients with schizophrenia (6-week duration), the aggregated incidence of extrapyramidal symptoms was 12.9% for SEROQUEL and 5.3% for placebo, though the incidence of the individual adverse events (akathisia, tremor, extrapyramidal disorder, hypokinesia, restlessness, psychomotor hyperactivity, muscle rigidity, dyskinesia) did not exceed 4.1% in any treatment group. In a short-term placebo-controlled monotherapy trial in children and adolescent patients with bipolar mania (3-week duration), the aggregated incidence of extrapyramidal symptoms was 3.6% for SEROQUEL and 1.1% for placebo.

Table 15 below presents a listing of patients with AEs potentially associated with EPS in the short-term placebo-controlled monotherapy trial in adolescent patients with schizophrenia (6-week duration).

Table 15: Adverse experiences potentially associated with EPS in the short-term placebo-controlled monotherapy trial in adolescent patients with schizophrenia (6-week duration)
Preferred Term | Placebo (N=75) |  | SEROQUEL 400 mg/day (N=73) |  | SEROQUEL 800 mg/day (N=74) |  | All SEROQUEL (N=147)
 | n | % | n | % | n | % | n | %
Dystonic event | 0 | 0.0 | 2 | 2.7 | 0 | 0.0 | 2 | 1.4
Parkinsonism | 2 | 2.7 | 4 | 5.5 | 4 | 5.4 | 8 | 5.4
Akathisia | 3 | 4.0 | 3 | 4.1 | 4 | 5.4 | 7 | 4.8
Dyskinetic event | 0 | 0.0 | 2 | 2.7 | 0 | 0.0 | 2 | 1.4
Other Extrapyramidal Events | 0 | 0.0 | 2 | 2.7 | 2 | 2.7 | 4 | 2.7

Table 16 below presents a listing of patients with Adverse Experiences potentially associated with EPS in a short-term placebo-controlled monotherapy trial in children and adolescent patients with bipolar mania (3-week duration).

Table 16: Adverse experiences potentially associated with EPS in a short-term placebo-controlled monotherapy trial in children and adolescent patients with bipolar mania (3-week duration)
Preferred Term | Placebo (N=90) |  | SEROQUEL 400 mg/day (N=95) |  | SEROQUEL 600 mg/day (N=98) |  | All SEROQUEL (N=193)
 | n | % | n | % | n | % | n | %
Parkinsonism | 1 | 1.1 | 2 | 2.1 | 1 | 1.0 | 3 | 1.6
Akathisia | 0 | 0.0 | 1 | 1.0 | 1 | 1.0 | 2 | 1.0
Other; Extrapyramidal Events | 0 | 0.0 | 1 | 1.1 | 1 | 1.0 | 2 | 1.0

Adverse Reactions in Long-Term Open-Label Trial

The adverse reactions reported in a 26-week, open-label trial with SEROQUEL in 5% or greater of the children and adolescent patients with schizophrenia or bipolar mania were somnolence (30%), headache (19%), vomiting (11%), increased weight (13%), insomnia (8%), nausea (10%), fatigue (8%), dizziness (9%), increased appetite (7%), upper respiratory tract infection (7%), agitation (5%), tachycardia (5%), and irritability (5%).

Other Adverse Reactions Observed During the Pre-Marketing Evaluation of SEROQUEL

Following is a list of COSTART terms that reflect treatment-emergent adverse reactions as defined in the introduction to the ADVERSE REACTIONS section reported by patients treated with SEROQUEL at multiple doses > 75 mg/day during any phase of a trial within the premarketing database of approximately 2200 patients treated for schizophrenia. All reported reactions are included except those already listed in the tables or elsewhere in labeling, those reactions for which a drug cause was remote, and those reaction terms which were so general as to be uninformative. It is important to emphasize that, although the reactions reported occurred during treatment with SEROQUEL, they were not necessarily caused by it.

Reactions are further categorized by body system and listed in order of decreasing frequency according to the following definitions: frequent adverse reactions are those occurring in at least 1/100 patients (only those not already listed in the tabulated results from placebo-controlled trials appear in this listing); infrequent adverse reactions are those occurring in 1/100 to 1/1000 patients; rare reactions are those occurring in fewer than 1/1000 patients.

Nervous System: Infrequent: abnormal dreams, dyskinesia, thinking abnormal, tardive dyskinesia, vertigo, involuntary movements, confusion, amnesia, psychosis, hallucinations, hyperkinesia, libido increased [adjusted for gender] , urinary retention, incoordination, paranoid reaction, abnormal gait, myoclonus, delusions, manic reaction, apathy, ataxia, depersonalization, stupor, bruxism, catatonic reaction, hemiplegia; Rare: aphasia, buccoglossal syndrome, choreoathetosis, delirium, emotional lability, euphoria, libido decreased*, neuralgia, stuttering, subdural hematoma.

Body as a Whole: Frequent: flu syndrome; Infrequent: neck pain, pelvic pain, suicide attempt, malaise, photosensitivity reaction, chills, face edema, moniliasis; Rare: abdomen enlarged.

Digestive System: Frequent: anorexia; Infrequent: increased salivation, increased appetite, gamma glutamyl transpeptidase increased, gingivitis, dysphagia, flatulence, gastroenteritis, gastritis, hemorrhoids, stomatitis, thirst, tooth caries, fecal incontinence, gastroesophageal reflux, gum hemorrhage, mouth ulceration, rectal hemorrhage, tongue edema; Rare: glossitis, hematemesis, intestinal obstruction, melena, pancreatitis.

Cardiovascular System: Infrequent: vasodilatation, QT interval prolonged, migraine, bradycardia, cerebral ischemia, irregular pulse, T wave abnormality, bundle branch block, cerebrovascular accident, deep thrombophlebitis, T wave inversion; Rare: angina pectoris, atrial fibrillation, AV block first degree, congestive heart failure, ST elevated, thrombophlebitis, T wave flattening, ST abnormality, increased QRS duration.

Respiratory System: Frequent: cough increased, dyspnea; Infrequent: pneumonia, epistaxis, asthma; Rare: hiccup, hyperventilation.

Metabolic and Nutritional System: Infrequent: weight loss, alkaline phosphatase increased, hyperlipemia, alcohol intolerance, dehydration, hyperglycemia, creatinine increased, hypoglycemia; Rare: glycosuria, gout, hand edema, hypokalemia, water intoxication.

Skin and Appendages System: Infrequent: pruritus, acne, eczema, contact dermatitis, maculopapular rash, seborrhea, skin ulcer; Rare: exfoliative dermatitis, psoriasis, skin discoloration.

Urogenital System: Infrequent: dysmenorrhea, vaginitis, urinary incontinence, metrorrhagia, impotence, dysuria, vaginal moniliasis, abnormal ejaculation, cystitis, urinary frequency, amenorrhea, female lactation, leukorrhea, vaginal hemorrhage, vulvovaginitis orchitis; Rare: gynecomastia, nocturia, polyuria, acute kidney failure.

Special Senses: Infrequent: conjunctivitis, abnormal vision, dry eyes, tinnitus, taste perversion, blepharitis, eye pain; Rare: abnormality of accommodation, deafness, glaucoma.

Musculoskeletal System: Infrequent: pathological fracture, myasthenia, twitching, arthralgia, arthritis, leg cramps, bone pain.

Hemic and Lymphatic System: Infrequent: leukocytosis, anemia, ecchymosis, eosinophilia, hypochromic anemia; lymphadenopathy, cyanosis; Rare: hemolysis, thrombocytopenia.

Endocrine System: Infrequent: hypothyroidism, diabetes mellitus; Rare: hyperthyroidism.

6.2 Vital Signs and Laboratory Values

Hyperglycemia, hyperlipidemia, weight gain, orthostatic hypotension and changes in thyroid hormone levels have been reported with quetiapine. Increases in blood pressure have also been reported with quetiapine in children and adolescents [see Warnings and Precautions (5.4, 5.5, 5.6, 5.8, 5.9 and 5.14)].

Neutrophil Counts

In placebo-controlled monotherapy clinical trials involving 3368 patients on quetiapine fumarate and 1515 on placebo, the incidence of at least one occurrence of neutrophil count <1.0 x 10^9/L among patients with a normal baseline neutrophil count and at least one available follow up laboratory measurement was 0.3% (10/2967) in patients treated with quetiapine fumarate, compared to 0.1% (2/1349) in patients treated with placebo. Patients with a pre-existing low WBC or a history of drug induced leukopenia/neutropenia should have their complete blood count (CBC) monitored frequently during the first few months of therapy and should discontinue SEROQUEL at the first sign of a decline in WBC in absence of other causative factors [see Warnings and Precautions (5.10)].

Decreased Hemoglobin

In short-term placebo-controlled trials, decreases in hemoglobin to ≤ 13 g/dL males, ≤ 12 g/dL females on at least one occasion occurred in 8.3% (594/7155) of quetiapine-treated patients compared to 6.2% (219/3536) of patients treated with placebo. In a database of controlled and uncontrolled clinical trials, decreases in hemoglobin to ≤ 13 g/dL males, ≤ 12 g/dL females on at least one occasion occurred in 11% (2277/20729) of quetiapine-treated patients.

ECG Changes

Adults: Between-group comparisons for pooled placebo-controlled trials revealed no statistically significant SEROQUEL/placebo differences in the proportions of patients experiencing potentially important changes in ECG parameters, including QT, QTc, and PR intervals. However, the proportions of patients meeting the criteria for tachycardia were compared in four 3- to 6-week placebo-controlled clinical trials for the treatment of schizophrenia revealing a 1% (4/399) incidence for SEROQUEL compared to 0.6% (1/156) incidence for placebo. In acute (monotherapy) bipolar mania trials the proportions of patients meeting the criteria for tachycardia was 0.5% (1/192) for SEROQUEL compared to 0% (0/178) incidence for placebo. In acute bipolar mania (adjunct) trials the proportions of patients meeting the same criteria was 0.6% (1/166) for SEROQUEL compared to 0% (0/171) incidence for placebo. In bipolar depression trials, no patients had heart rate increases to > 120 beats per minute. SEROQUEL use was associated with a mean increase in heart rate, assessed by ECG, of 7 beats per minute compared to a mean increase of 1 beat per minute among placebo patients. This slight tendency to tachycardia in adults may be related to SEROQUEL's potential for inducing orthostatic changes [see Warnings and Precautions (5.8)].

Children and Adolescents: In the acute (6 week) schizophrenia trial in adolescents, potentially clinically significant increases in heart rate (> 110 bpm) occurred in 5.2% (3/73) of patients receiving SEROQUEL 400 mg and 8.5% (5/74) of patients receiving SEROQUEL 800 mg compared to 0% (0/75) of patients receiving placebo. Mean increases in heart rate were 3.8 bpm and 11.2 bpm for SEROQUEL 400 mg and 800 mg groups, respectively, compared to a decrease of 3.3 bpm in the placebo group [see Warnings and Precautions (5.8)].

In the acute (3 week) bipolar mania trial in children and adolescents, potentially clinically significant increases in heart rate (> 110 bpm) occurred in 1.1% (1/95) of patients receiving SEROQUEL 400 mg and 2.4% (2/98) of patients receiving SEROQUEL 600 mg compared to 0% (0/98) of patients receiving placebo. Mean increases in heart rate were 12.8 bpm and 13.4 bpm for SEROQUEL 400 mg and 600 mg groups, respectively, compared to a decrease of 1.7 bpm in the placebo group [see Warnings and Precautions (5.8)].

6.3 Post Marketing Experience

The following adverse reactions were identified during post approval of SEROQUEL. Because these reactions are reported voluntarily from a population of uncertain size, it is not always possible to reliably estimate their frequency or establish a causal relationship to drug exposure.

Adverse reactions reported since market introduction which were temporally related to SEROQUEL therapy include: anaphylactic reaction and galactorrhea.

Other adverse reactions reported since market introduction, which were temporally related to SEROQUEL therapy, but not necessarily causally related, include the following: agranulocytosis, cardiomyopathy, hyponatremia, myocarditis, rhabdomyolysis, syndrome of inappropriate antidiuretic hormone secretion (SIADH), Stevens-Johnson syndrome (SJS), and decreased platelets.

In post-marketing clinical trials, elevations in total cholesterol (predominantly LDL cholesterol), somnambulism (and other related events) and hypothermia have been reported.

7 DRUG INTERACTIONS

The risks of using SEROQUEL in combination with other drugs have not been extensively evaluated in systematic studies. Given the primary CNS effects of SEROQUEL, caution should be used when it is taken in combination with other centrally acting drugs. SEROQUEL potentiated the cognitive and motor effects of alcohol in a clinical trial in subjects with selected psychotic disorders, and alcoholic beverages should be avoided while taking SEROQUEL.

Because of its potential for inducing hypotension, SEROQUEL may enhance the effects of certain antihypertensive agents.

SEROQUEL may antagonize the effects of levodopa and dopamine agonists.

The use of quetiapine should be avoided in combination with drugs known to increase QT interval, and caution should be exercised when quetiapine is used in combination with drugs known to cause electrolyte imbalance [see Warnings and Precautions (5.12)].

There have been literature reports suggesting false positive results in urine enzyme immunoassays for methadone and tricyclic antidepressants in patients who have taken quetiapine. Caution should be exercised in the interpretation of positive urine drug screen results for these drugs, and confirmation by alternative analytical technique (e.g. chromatographic methods) should be considered.

7.1 The Effect of Other Drugs on Quetiapine

Phenytoin: Coadministration of quetiapine (250 mg three times daily) and phenytoin (100 mg three times daily) increased the mean oral clearance of quetiapine by 5-fold. Increased doses of SEROQUEL may be required to maintain control of symptoms of schizophrenia in patients receiving quetiapine and phenytoin, or other hepatic enzyme inducers (e.g., carbamazepine, barbiturates, rifampin, glucocorticoids). Caution should be taken if phenytoin is withdrawn and replaced with a non-inducer (e.g., valproate) [see Dosage and Administration (2)].

Divalproex: Coadministration of quetiapine (150 mg twice daily) and divalproex (500 mg twice daily) increased the mean maximum plasma concentration of quetiapine at steady state by 17% without affecting the extent of absorption or mean oral clearance.

Thioridazine: Thioridazine (200 mg twice daily) increased the oral clearance of quetiapine (300 mg twice daily) by 65%.

Cimetidine: Administration of multiple daily doses of cimetidine (400 mg three times daily for 4 days) resulted in a 20% decrease in the mean oral clearance of quetiapine (150 mg three times daily). Dosage adjustment for quetiapine is not required when it is given with cimetidine.

P450 3A Inhibitors: Coadministration of ketoconazole (200 mg once daily for 4 days), a potent inhibitor of cytochrome P450 3A, reduced oral clearance of quetiapine by 84%, resulting in a 335% increase in maximum plasma concentration of quetiapine. Caution (reduced dosage) is indicated when SEROQUEL is administered with ketoconazole and other inhibitors of cytochrome P450 3A (e.g., itraconazole, fluconazole, erythromycin, and protease inhibitors).

Fluoxetine, Imipramine, Haloperidol, and Risperidone: Coadministration of fluoxetine (60 mg once daily), imipramine (75 mg twice daily), haloperidol (7.5 mg twice daily), or risperidone (3 mg twice daily) with quetiapine (300 mg twice daily) did not alter the steady-state pharmacokinetics of quetiapine.

7.2 Effect of Quetiapine on Other Drugs

Lorazepam: The mean oral clearance of lorazepam (2 mg, single dose) was reduced by 20% in the presence of quetiapine administered as 250 mg three times daily dosing.

Divalproex: The mean maximum concentration and extent of absorption of total and free valproic acid at steady state were decreased by 10 to 12% when divalproex (500 mg twice daily) was administered with quetiapine (150 mg twice daily). The mean oral clearance of total valproic acid (administered as divalproex 500 mg twice daily) was increased by 11% in the presence of quetiapine (150 mg twice daily). The changes were not significant.

Lithium: Concomitant administration of quetiapine (250 mg three times daily) with lithium had no effect on any of the steady-state pharmacokinetic parameters of lithium.

Antipyrine: Administration of multiple daily doses up to 750 mg/day (on a three times daily schedule) of quetiapine to subjects with selected psychotic disorders had no clinically relevant effect on the clearance of antipyrine or urinary recovery of antipyrine metabolites. These results indicate that quetiapine does not significantly induce hepatic enzymes responsible for cytochrome P450 mediated metabolism of antipyrine.

8 USE IN SPECIFIC POPULATIONS

8.1 Pregnancy

Pregnancy Category C:

There are no adequate and well-controlled studies of SEROQUEL use in pregnant women. In limited published literature, there were no major malformations associated with quetiapine exposure during pregnancy. In animal studies, embryo-fetal toxicity occurred. Quetiapine should be used during pregnancy only if the potential benefit justifies the potential risk to the fetus.

There are limited published data on the use of quetiapine for treatment of schizophrenia and other psychiatric disorders during pregnancy. In a prospective observational study, 21 women exposed to quetiapine and other psychoactive medications during pregnancy delivered infants with no major malformations. Among 42 other infants born to pregnant women who used quetiapine during pregnancy, there were no major malformations reported (one study of 36 women, 6 case reports). Due to the limited number of exposed pregnancies, these postmarketing data do not reliably estimate the frequency or absence of adverse outcomes.

When pregnant rats and rabbits were exposed to quetiapine during organogenesis, there was no increase in the incidence of major malformations in fetuses at doses up to 2.4 times the maximum recommended human dose for schizophrenia (MRHD, 800 mg/day on a mg/m^2 basis); however, there was evidence of embryo-fetal toxicity. In rats, delays in skeletal ossification occurred at 0.6 and 2.4 times the MRHD and in rabbits at 1.2 and 2.4 times the MRHD. At 2.4 times the MRHD, there was an increased incidence of carpal/tarsal flexure (minor soft tissue anomaly) in rabbit fetuses and decreased fetal weights in both species. Maternal toxicity (decreased body weights and/or death) occurred at 2.4 times the MRHD in rats and at 0.6-2.4 times the MRHD (all doses) in rabbits.

In a peri/postnatal reproductive study in rats, no drug-related effects were observed when pregnant dams were treated with quetiapine at doses 0.01, 0.12, and 0.24 times the MRHD. However, in a preliminary peri/postnatal study, there were increases in fetal and pup death, and decreases in mean litter weight at 3.0 times the MRHD.

Non-Teratogenic Effects

Neonates exposed to antipsychotic drugs (including SEROQUEL), during the third trimester of pregnancy are at risk for extrapyramidal and/or withdrawal symptoms following delivery. There have been reports of agitation, hypertonia, hypotonia, tremor, somnolence, respiratory distress and feeding disorder in these neonates. These complications have varied in severity; while in some cases symptoms have been self-limited, in other cases neonates have required intensive care unit support and prolonged hospitalization.

SEROQUEL should be used during pregnancy only if the potential benefit justifies the potential risk to the fetus.

8.2 Labor and Delivery

The effect of SEROQUEL on labor and delivery in humans is unknown.

8.3 Nursing Mothers

SEROQUEL was excreted into human milk. It is recommended that women receiving SEROQUEL should not breast feed.

In published case reports, the level of quetiapine in breast milk ranged from undetectable to 170 μg/L. The estimated infant dose ranged from 0.09% to 0.43% of the weight-adjusted maternal dose. Based on a limited number (N=8) of mother/infant pairs, calculated infant daily doses range from less than 0.01 mg/kg (at a maternal daily dose up to 100 mg quetiapine) to 0.1 mg/kg (at a maternal daily dose of 400 mg).

8.4 Pediatric Use

In general, the adverse reactions observed in children and adolescents during the clinical trials were similar to those in the adult population with few exceptions. Increases in systolic and diastolic blood pressure occurred in children and adolescents and did not occur in adults. Orthostatic hypotension occurred more frequently in adults (4-7%) compared to children and adolescents (< 1%).

Schizophrenia

The efficacy and safety of SEROQUEL in the treatment of schizophrenia in adolescents aged 13 to 17 years were demonstrated in one 6–week, double-blind, placebo-controlled trial [see Indications and Usage (1.1), Dosage and Administration (2.1), Adverse Reactions (6.1), and Clinical Studies (14.1)].

Safety and effectiveness of SEROQUEL in pediatric patients less than 13 years of age with schizophrenia have not been established.

Maintenance

The safety and effectiveness of SEROQUEL in the maintenance treatment of bipolar disorder has not been established in pediatric patients less than 18 years of age. The safety and effectiveness of SEROQUEL in the maintenance treatment of schizophrenia has not been established in any patient population, including pediatric patients.

Bipolar Mania

The efficacy and safety of SEROQUEL in the treatment of mania in children and adolescents ages 10 to 17 years with Bipolar I disorder was demonstrated in a 3-week, double-blind, placebo controlled, multicenter trial [see Indications and Usage (1.2), Dosage and Administration (2.2), Adverse Reactions (6.1), and Clinical Studies (14.2)].

Safety and effectiveness of SEROQUEL in pediatric patients less than 10 years of age with bipolar mania have not been established.

Bipolar Depression

Safety and effectiveness of SEROQUEL in pediatric patients less than 18 years of age with bipolar depression have not been established.

Some differences in the pharmacokinetics of quetiapine were noted between children/adolescents (10 to 17 years of age) and adults. When adjusted for weight, the AUC and Cmax of quetiapine were 41% and 39% lower, respectively, in children and adolescents compared to adults. The pharmacokinetics of the active metabolite, norquetiapine, were similar between children/adolescents and adults after adjusting for weight [see Clinical Pharmacology (12.3)].

8.5 Geriatric Use

Of the approximately 3700 patients in clinical studies with SEROQUEL, 7% (232) were 65 years of age or over. In general, there was no indication of any different tolerability of SEROQUEL in the elderly compared to younger adults. Nevertheless, the presence of factors that might decrease pharmacokinetic clearance, increase the pharmacodynamic response to SEROQUEL, or cause poorer tolerance or orthostasis, should lead to consideration of a lower starting dose, slower titration, and careful monitoring during the initial dosing period in the elderly. The mean plasma clearance of SEROQUEL was reduced by 30% to 50% in elderly patients when compared to younger patients [see Clinical Pharmacology (12) and Dosage and Administration (2)].

9 DRUG ABUSE AND DEPENDENCE

9.1 Controlled Substance

SEROQUEL is not a controlled substance.

9.2 Abuse

SEROQUEL has not been systematically studied, in animals or humans, for its potential for abuse, tolerance or physical dependence. While the clinical trials did not reveal any tendency for any drug-seeking behavior, these observations were not systematic and it is not possible to predict on the basis of this limited experience the extent to which a CNS-active drug will be misused, diverted, and/or abused once marketed. Consequently, patients should be evaluated carefully for a history of drug abuse, and such patients should be observed closely for signs of misuse or abuse of SEROQUEL, e.g., development of tolerance, increases in dose, drug-seeking behavior.

10 OVERDOSAGE

10.1 Human Experience

In clinical trials, survival has been reported in acute overdoses of up to 30 grams of quetiapine. Most patients who overdosed experienced no adverse reactions or recovered fully from the reported reactions. Death has been reported in a clinical trial following an overdose of 13.6 grams of quetiapine alone. In general, reported signs and symptoms were those resulting from an exaggeration of the drugs known pharmacological effects, ie, drowsiness and sedation, tachycardia and hypotension. Patients with pre-existing severe cardiovascular disease may be at an increased risk of the effects of overdose [see Warnings and Precautions (5.12)]. One case, involving an estimated overdose of 9600 mg, was associated with hypokalemia and first degree heart block. In post-marketing experience, there were cases reported of QT prolongation with overdose. There were also very rare reports of overdose of SEROQUEL alone resulting in death or coma.

10.2 Management of Overdosage

In case of acute overdosage, establish and maintain an airway and ensure adequate oxygenation and ventilation. Gastric lavage (after intubation, if patient is unconscious) and administration of activated charcoal together with a laxative should be considered. The possibility of obtundation, seizure or dystonic reaction of the head and neck following overdose may create a risk of aspiration with induced emesis. Cardiovascular monitoring should commence immediately and should include continuous electrocardiographic monitoring to detect possible arrhythmias. If antiarrhythmic therapy is administered, disopyramide, procainamide and quinidine carry a theoretical hazard of additive QT-prolonging effects when administered in patients with acute overdosage of SEROQUEL. Similarly it is reasonable to expect that the alpha-adrenergic-blocking properties of bretylium might be additive to those of quetiapine, resulting in problematic hypotension.

There is no specific antidote to SEROQUEL. Therefore, appropriate supportive measures should be instituted. The possibility of multiple drug involvement should be considered. Hypotension and circulatory collapse should be treated with appropriate measures such as intravenous fluids and/or sympathomimetic agents (epinephrine and dopamine should not be used, since beta stimulation may worsen hypotension in the setting of quetiapine-induced alpha blockade). In cases of severe extrapyramidal symptoms, anticholinergic medication should be administered. Close medical supervision and monitoring should continue until the patient recovers.

11 DESCRIPTION

SEROQUEL® (quetiapine fumarate) is a psychotropic agent belonging to a chemical class, the dibenzothiazepine derivatives. The chemical designation is 2-[2-(4-dibenzo [b,f ] [1,4]thiazepin-11-yl-1-piperazinyl)ethoxy]-ethanol fumarate (2:1) (salt). It is present in tablets as the fumarate salt. All doses and tablet strengths are expressed as milligrams of base, not as fumarate salt. Its molecular formula is C42H50N6O4S2•C4H4O4 and it has a molecular weight of 883.11 (fumarate salt). The structural formula is:

Quetiapine fumarate is a white to off-white crystalline powder which is moderately soluble in water.

SEROQUEL is supplied for oral administration as 25 mg (round, peach), 50 mg (round, white), 100 mg (round, yellow), 200 mg (round, white), 300 mg (capsule-shaped, white), and 400 mg (capsule-shaped, yellow) tablets.

Inactive ingredients are povidone, dibasic dicalcium phosphate dihydrate, microcrystalline cellulose, sodium starch glycolate, lactose monohydrate, magnesium stearate, hypromellose, polyethylene glycol and titanium dioxide.

The 25 mg tablets contain red ferric oxide and yellow ferric oxide and the 100 mg and 400 mg tablets contain only yellow ferric oxide.

12 CLINICAL PHARMACOLOGY

12.1 Mechanism of Action

The mechanism of action of SEROQUEL, as with other drugs having efficacy in the treatment of schizophrenia and bipolar disorder, is unknown. However, it has been proposed that the efficacy of SEROQUEL in schizophrenia and its mood stabilizing properties in bipolar depression and mania are mediated through a combination of dopamine type 2 (D2) and serotonin type 2 (5HT2) antagonism. Antagonism at receptors other than dopamine and 5HT2 with similar receptor affinities may explain some of the other effects of SEROQUEL.

SEROQUEL’s antagonism of histamine H1 receptors may explain the somnolence observed with this drug.

SEROQUEL’s antagonism of adrenergic α1 receptors may explain the orthostatic hypotension observed with this drug.

12.2 Pharmacodynamics

SEROQUEL is an antagonist at multiple neurotransmitter receptors in the brain: serotonin 5HT1A and 5HT2 (IC50s=717 & 148nM, respectively), dopamine D1 and D2 (IC50s=1268 & 329nM, respectively), histamine H1 (IC50=30nM), and adrenergic α1 and α2 receptors (IC50s=94 & 271nM, respectively). SEROQUEL has no appreciable affinity at cholinergic muscarinic and benzodiazepine receptors (IC50s>5000 nM).

12.3 Pharmacokinetics

Adults

Quetiapine fumarate activity is primarily due to the parent drug. The multiple-dose pharmacokinetics of quetiapine are dose-proportional within the proposed clinical dose range, and quetiapine accumulation is predictable upon multiple dosing. Elimination of quetiapine is mainly via hepatic metabolism with a mean terminal half-life of about 6 hours within the proposed clinical dose range. Steady-state concentrations are expected to be achieved within two days of dosing. Quetiapine is unlikely to interfere with the metabolism of drugs metabolized by cytochrome P450 enzymes.

Children and Adolescents

At steady-state the pharmacokinetics of the parent compound, in children and adolescents (10-17 years of age), were similar to adults. However, when adjusted for dose and weight, AUC and Cmax of the parent compound were 41% and 39% lower, respectively, in children and adolescents than in adults. For the active metabolite, norquetiapine, AUC and Cmax were 45% and 31% higher, respectively, in children and adolescents than in adults. When adjusted for dose and weight, the pharmacokinetics of the metabolite, norquetiapine, was similar between children and adolescents and adults [see Use in Specific Populations (8.4)].

Absorption

Quetiapine fumarate is rapidly absorbed after oral administration, reaching peak plasma concentrations in 1.5 hours. The tablet formulation is 100% bioavailable relative to solution. The bioavailability of quetiapine is marginally affected by administration with food, with Cmax and AUC values increased by 25% and 15%, respectively.

Distribution

Quetiapine is widely distributed throughout the body with an apparent volume of distribution of 10±4 L/kg. It is 83% bound to plasma proteins at therapeutic concentrations. In vitro, quetiapine did not affect the binding of warfarin or diazepam to human serum albumin. In turn, neither warfarin nor diazepam altered the binding of quetiapine.

Metabolism and Elimination

Following a single oral dose of ^14C-quetiapine, less than 1% of the administered dose was excreted as unchanged drug, indicating that quetiapine is highly metabolized. Approximately 73% and 20% of the dose was recovered in the urine and feces, respectively.

Quetiapine is extensively metabolized by the liver. The major metabolic pathways are sulfoxidation to the sulfoxide metabolite and oxidation to the parent acid metabolite; both metabolites are pharmacologically inactive. In vitro studies using human liver microsomes revealed that the cytochrome P450 3A4 isoenzyme is involved in the metabolism of quetiapine to its major, but inactive, sulfoxide metabolite and in the metabolism of its active metabolite N-desalkyl quetiapine.

Age

Oral clearance of quetiapine was reduced by 40% in elderly patients (≥ 65 years, n=9) compared to young patients (n=12), and dosing adjustment may be necessary [see Dosage and Administration (2)].

Gender

There is no gender effect on the pharmacokinetics of quetiapine.

Race

There is no race effect on the pharmacokinetics of quetiapine.

Smoking

Smoking has no effect on the oral clearance of quetiapine.

Renal Insufficiency

Patients with severe renal impairment (Clcr=10-30 mL/min/1.73 m^2, n=8) had a 25% lower mean oral clearance than normal subjects (Clcr > 80 mL/min/1.73 m^2, n=8), but plasma quetiapine concentrations in the subjects with renal insufficiency were within the range of concentrations seen in normal subjects receiving the same dose. Dosage adjustment is therefore not needed in these patients.

Hepatic Insufficiency

Hepatically impaired patients (n=8) had a 30% lower mean oral clearance of quetiapine than normal subjects. In two of the 8 hepatically impaired patients, AUC and Cmax were 3 times higher than those observed typically in healthy subjects. Since quetiapine is extensively metabolized by the liver, higher plasma levels are expected in the hepatically impaired population, and dosage adjustment may be needed [see Dosage and Administration (2)].

Drug-Drug Interactions

In vitro enzyme inhibition data suggest that quetiapine and 9 of its metabolites would have little inhibitory effect on in vivo metabolism mediated by cytochromes P450 1A2, 2C9, 2C19, 2D6 and 3A4.

Quetiapine oral clearance is increased by the prototype cytochrome P450 3A4 inducer, phenytoin, and decreased by the prototype cytochrome P450 3A4 inhibitor, ketoconazole. Dose adjustment of quetiapine will be necessary if it is coadministered with phenytoin or ketoconazole [see Drug Interactions (7.1)].

Quetiapine oral clearance is not inhibited by the non-specific enzyme inhibitor, cimetidine.

Quetiapine at doses of 750 mg/day did not affect the single dose pharmacokinetics of antipyrine, lithium or lorazepam [see Drug Interactions (7.2)].

13 NONCLINICAL TOXICOLOGY

13.1 Carcinogenesis, Mutagenesis, Impairment of Fertility

Carcinogenesis

Carcinogenicity studies were conducted in C57BL mice and Wistar rats. Quetiapine was administered in the diet to mice at doses of 20, 75, 250, and 750 mg/kg and to rats by gavage at doses of 25, 75, and 250 mg/kg for two years. These doses are equivalent to 0.1, 0.5, 1.5, and 4.5 times the maximum human dose (800 mg/day) on a mg/m^2 basis (mice) or 0.3, 0.9, and 3.0 times the maximum human dose on a mg/m^2 basis (rats). There were statistically significant increases in thyroid gland follicular adenomas in male mice at doses of 250 and 750 mg/kg or 1.5 and 4.5 times the maximum human dose on a mg/m^2 basis and in male rats at a dose of 250 mg/kg or 3.0 times the maximum human dose on a mg/m^2 basis. Mammary gland adenocarcinomas were statistically significantly increased in female rats at all doses tested (25, 75, and 250 mg/kg or 0.3, 0.9, and 3.0 times the maximum recommended human dose on a mg/m^2 basis).

Thyroid follicular cell adenomas may have resulted from chronic stimulation of the thyroid gland by thyroid stimulating hormone (TSH) resulting from enhanced metabolism and clearance of thyroxine by rodent liver. Changes in TSH, thyroxine, and thyroxine clearance consistent with this mechanism were observed in subchronic toxicity studies in rat and mouse and in a 1-year toxicity study in rat; however, the results of these studies were not definitive. The relevance of the increases in thyroid follicular cell adenomas to human risk, through whatever mechanism, is unknown.

Antipsychotic drugs have been shown to chronically elevate prolactin levels in rodents. Serum measurements in a 1-year toxicity study showed that quetiapine increased median serum prolactin levels a maximum of 32- and 13-fold in male and female rats, respectively. Increases in mammary neoplasms have been found in rodents after chronic administration of other antipsychotic drugs and are considered to be prolactin-mediated. The relevance of this increased incidence of prolactin-mediated mammary gland tumors in rats to human risk is unknown [see Warnings and Precautions (5.15)].

Mutagenesis

The mutagenic potential of quetiapine was tested in six in vitro bacterial gene mutation assays and in an in vitro mammalian gene mutation assay in Chinese Hamster Ovary cells. However, sufficiently high concentrations of quetiapine may not have been used for all tester strains. Quetiapine did produce a reproducible increase in mutations in one Salmonella typhimurium tester strain in the presence of metabolic activation. No evidence of clastogenic potential was obtained in an in vitro chromosomal aberration assay in cultured human lymphocytes or in the in vivo micronucleus assay in rats.

Impairment of Fertility

Quetiapine decreased mating and fertility in male Sprague-Dawley rats at oral doses of 50 and 150 mg/kg or 0.6 and 1.8 times the maximum human dose on a mg/m^2 basis. Drug-related effects included increases in interval to mate and in the number of matings required for successful impregnation. These effects continued to be observed at 150 mg/kg even after a two-week period without treatment. The no-effect dose for impaired mating and fertility in male rats was 25 mg/kg, or 0.3 times the maximum human dose on a mg/m^2 basis. Quetiapine adversely affected mating and fertility in female Sprague-Dawley rats at an oral dose of 50 mg/kg, or 0.6 times the maximum human dose on a mg/m^2 basis. Drug-related effects included decreases in matings and in matings resulting in pregnancy, and an increase in the interval to mate. An increase in irregular estrus cycles was observed at doses of 10 and 50 mg/kg, or 0.1 and 0.6 times the maximum human dose on a mg/m^2 basis. The no-effect dose in female rats was 1 mg/kg, or 0.01 times the maximum human dose on a mg/m^2 basis.

13.2 Animal Toxicology

Quetiapine caused a dose-related increase in pigment deposition in thyroid gland in rat toxicity studies which were 4 weeks in duration or longer and in a mouse 2–year carcinogenicity study. Doses were 10-250 mg/kg in rats, 75-750 mg/kg in mice; these doses are 0.1-3.0, and 0.1-4.5 times the maximum recommended human dose (on a mg/m^2 basis), respectively. Pigment deposition was shown to be irreversible in rats. The identity of the pigment could not be determined, but was found to be co-localized with quetiapine in thyroid gland follicular epithelial cells. The functional effects and the relevance of this finding to human risk are unknown.

In dogs receiving quetiapine for 6 or 12 months, but not for 1 month, focal triangular cataracts occurred at the junction of posterior sutures in the outer cortex of the lens at a dose of 100 mg/kg, or 4 times the maximum recommended human dose on a mg/m^2 basis. This finding may be due to inhibition of cholesterol biosynthesis by quetiapine. Quetiapine caused a dose-related reduction in plasma cholesterol levels in repeat-dose dog and monkey studies; however, there was no correlation between plasma cholesterol and the presence of cataracts in individual dogs. The appearance of delta–8–cholestanol in plasma is consistent with inhibition of a late stage in cholesterol biosynthesis in these species. There also was a 25% reduction in cholesterol content of the outer cortex of the lens observed in a special study in quetiapine treated female dogs. Drug-related cataracts have not been seen in any other species; however, in a 1-year study in monkeys, a striated appearance of the anterior lens surface was detected in 2/7 females at a dose of 225 mg/kg or 5.5 times the maximum recommended human dose on a mg/m^2 basis.

14 CLINICAL STUDIES

14.1 Schizophrenia

Adults

The efficacy of SEROQUEL in the treatment of schizophrenia was established in 3 short-term (6-week) controlled trials of inpatients with schizophrenia who met DSM III-R criteria for schizophrenia. Although a single fixed dose haloperidol arm was included as a comparative treatment in one of the three trials, this single haloperidol dose group was inadequate to provide a reliable and valid comparison of SEROQUEL and haloperidol.

Several instruments were used for assessing psychiatric signs and symptoms in these studies, among them the Brief Psychiatric Rating Scale (BPRS), a multi-item inventory of general psychopathology traditionally used to evaluate the effects of drug treatment in schizophrenia. The BPRS psychosis cluster (conceptual disorganization, hallucinatory behavior, suspiciousness, and unusual thought content) is considered a particularly useful subset for assessing actively psychotic schizophrenic patients. A second traditional assessment, the Clinical Global Impression (CGI), reflects the impression of a skilled observer, fully familiar with the manifestations of schizophrenia, about the overall clinical state of the patient.

The results of the trials follow:

1. In a 6-week, placebo-controlled trial (n=361) involving 5 fixed doses of SEROQUEL (75 mg/day, 150 mg/day, 300 mg/day, 600 mg/day and 750 mg/day given in divided doses three times per day), the 4 highest doses of SEROQUEL were generally superior to placebo on the BPRS total score, the BPRS psychosis cluster and the CGI severity score, with the maximal effect seen at 300 mg/day, and the effects of doses of 150 mg/day to 750 mg/day were generally indistinguishable.
2. In a 6-week, placebo-controlled trial (n=286) involving titration of SEROQUEL in high (up to 750 mg/day given in divided doses three times per day) and low (up to 250 mg/day given in divided doses three times per day) doses, only the high dose SEROQUEL group (mean dose, 500 mg/day) was superior to placebo on the BPRS total score, the BPRS psychosis cluster, and the CGI severity score.
3. In a 6-week dose and dose regimen comparison trial (n=618) involving two fixed doses of SEROQUEL (450 mg/day given in divided doses both twice daily and three times daily and 50 mg/day given in divided doses twice daily), only the 450 mg/day (225 mg given twice daily) dose group was superior to the 50 mg/day (25 mg given twice daily) SEROQUEL dose group on the BPRS total score, the BPRS psychosis cluster, and the CGI severity score.

Examination of population subsets (race, gender, and age) did not reveal any differential responsiveness on the basis of race or gender, with an apparently greater effect in patients under the age of 40 years compared to those older than 40. The clinical significance of this finding is unknown.

Adolescents (ages 13-17)

The efficacy of SEROQUEL in the treatment of schizophrenia in adolescents (13–17 years of age) was demonstrated in a 6–week, double-blind, placebo-controlled trial. Patients who met DSM-IV diagnostic criteria for schizophrenia were randomized into one of three treatment groups: SEROQUEL 400 mg/day (n = 73), SEROQUEL 800 mg/day (n = 74), or placebo (n = 75). Study medication was initiated at 50 mg/day and on day 2 increased to 100 mg/per day (divided and given two or three times per day). Subsequently, the dose was titrated to the target dose of 400 mg/day or 800 mg/day using increments of 100 mg/day, divided and given two or three times daily. The primary efficacy variable was the mean change from baseline in total Positive and Negative Syndrome Scale (PANSS).

SEROQUEL at 400 mg/day and 800 mg/day was superior to placebo in the reduction of PANSS total score.

14.2 Bipolar Disorder

Manic Episodes

Adults

The efficacy of SEROQUEL in the acute treatment of manic episodes was established in 3 placebo-controlled trials in patients who met DSM-IV criteria for bipolar I disorder with manic episodes. These trials included patients with or without psychotic features and excluded patients with rapid cycling and mixed episodes. Of these trials, 2 were monotherapy (12 weeks) and 1 was adjunct therapy (3 weeks) to either lithium or divalproex. Key outcomes in these trials were change from baseline in the Young Mania Rating Scale (YMRS) score at 3 and 12 weeks for monotherapy and at 3 weeks for adjunct therapy. Adjunct therapy is defined as the simultaneous initiation or subsequent administration of SEROQUEL with lithium or divalproex.

The primary rating instrument used for assessing manic symptoms in these trials was YMRS, an 11-item clinician-rated scale traditionally used to assess the degree of manic symptomatology (irritability, disruptive/aggressive behavior, sleep, elevated mood, speech, increased activity, sexual interest, language/thought disorder, thought content, appearance, and insight) in a range from 0 (no manic features) to 60 (maximum score).

The results of the trials follow:

Monotherapy

The efficacy of SEROQUEL in the acute treatment of bipolar mania was established in 2 placebo-controlled trials. In two 12-week trials (n=300, n=299) comparing SEROQUEL to placebo, SEROQUEL was superior to placebo in the reduction of the YMRS total score at weeks 3 and 12. The majority of patients in these trials taking SEROQUEL were dosed in a range between 400 mg/day and 800 mg per day.

Adjunct Therapy

In this 3-week placebo-controlled trial, 170 patients with bipolar mania (YMRS > 20) were randomized to receive SEROQUEL or placebo as adjunct treatment to lithium or divalproex. Patients may or may not have received an adequate treatment course of lithium or divalproex prior to randomization. SEROQUEL was superior to placebo when added to lithium or divalproex alone in the reduction of YMRS total score.

The majority of patients in this trial taking SEROQUEL were dosed in a range between 400 mg/day and 800 mg per day. In a similarly designed trial (n=200), SEROQUEL was associated with an improvement in YMRS scores but did not demonstrate superiority to placebo, possibly due to a higher placebo effect.

Children and Adolescents (ages 10-17)

The efficacy of SEROQUEL in the acute treatment of manic episodes associated with bipolar I disorder in children and adolescents (10 to 17 years of age) was demonstrated in a 3-week, double-blind, placebo-controlled, multicenter trial. Patients who met DSM-IV diagnostic criteria for a manic episode were randomized into one of three treatment groups: SEROQUEL 400 mg/day (n = 95), SEROQUEL 600 mg/day (n = 98), or placebo (n = 91). Study medication was initiated at 50 mg/day and on day 2 increased to 100 mg/day (divided doses given two or three times daily). Subsequently, the dose was titrated to a target dose of 400 mg/day or 600 mg/day using increments of 100 mg/day, given in divided doses two or three times daily. The primary efficacy variable was the mean change from baseline in total YMRS score.

SEROQUEL 400 mg/day and 600 mg/day were superior to placebo in the reduction of YMRS total score.

Depressive Episodes

Adults

The efficacy of SEROQUEL for the acute treatment of depressive episodes associated with bipolar disorder was established in 2 identically designed 8-week, randomized, double-blind, placebo-controlled studies (N=1045). These studies included patients with either bipolar I or II disorder and those with or without a rapid cycling course. Patients randomized to SEROQUEL were administered fixed doses of either 300 mg or 600 mg once daily.

The primary rating instrument used to assess depressive symptoms in these studies was the Montgomery-Asberg Depression Rating Scale (MADRS), a 10–item clinician-rated scale with scores ranging from 0 to 60. The primary endpoint in both studies was the change from baseline in MADRS score at week 8. In both studies, SEROQUEL was superior to placebo in reduction of MADRS score. Improvement in symptoms, as measured by change in MADRS score relative to placebo, was seen in both studies at Day 8 (week 1) and onwards. In these studies, no additional benefit was seen with the 600 mg dose. For the 300 mg dose group, statistically significant improvements over placebo were seen in overall quality of life and satisfaction related to various areas of functioning, as measured using the Q-LES-Q(SF).

Maintenance Treatment as an Adjunct to Lithium or Divalproex

The efficacy of SEROQUEL in the maintenance treatment of bipolar I disorder was established in 2 placebo-controlled trials in patients (n=1326) who met DSM-IV criteria for bipolar I disorder. The trials included patients whose most recent episode was manic, depressed, or mixed, with or without psychotic features. In the open-label phase, patients were required to be stable on SEROQUEL plus lithium or divalproex for at least 12 weeks in order to be randomized. On average, patients were stabilized for 15 weeks. In the randomization phase, patients continued treatment with lithium or divalproex and were randomized to receive either SEROQUEL (administered twice daily totaling 400 mg/day to 800 mg/day) or placebo. Approximately 50% of the patients had discontinued from the SEROQUEL group by day 280 and 50% of the placebo group had discontinued by day 117 of double-blind treatment. The primary endpoint in these studies was time to recurrence of a mood event (manic, mixed or depressed episode). A mood event was defined as medication initiation or hospitalization for a mood episode; YMRS score ≥ 20 or MADRS score ≥ 20 at 2 consecutive assessments; or study discontinuation due to a mood event.

In both studies, SEROQUEL was superior to placebo in increasing the time to recurrence of any mood event. The treatment effect was present for increasing time to recurrence of both manic and depressed episodes. The effect of SEROQUEL was independent of any specific subgroup (assigned mood stabilizer, sex, age, race, most recent bipolar episode, or rapid cycling course).

16 HOW SUPPLIED/STORAGE AND HANDLING

25 mg Tablets peach, round, biconvex, film coated tablets, identified with 'SEROQUEL' and ‘25’ on one side and plain on the other side, are supplied in

Bottles of 10 | NDC 54868-4961-3
Bottles of 20 | NDC 54868-4961-1
Bottles of 30 | NDC 54868-4961-2
Bottles of 60 | NDC 54868-4961-0
Bottles of 90 | NDC 54868-4961-4

50 mg Tablets (NDC 0310-0278) white, round, biconvex, film coated tablets, identified with 'SEROQUEL' and ‘50’ on one side and plain on the other side, are supplied in

Bottles of 10 | NDC 54868-5581-3
Bottles of 20 | NDC 54868-5581-1
Bottles of 30 | NDC 54868-5581-2
Bottles of 60 | NDC 54868-5581-0

100 mg Tablets (NDC 0310-0271) yellow, round, biconvex film coated tablets, identified with 'SEROQUEL' and ‘100’ on one side and plain on the other side, are supplied in

Bottles of 10 | NDC 54868-4257-4
Bottles of 30 | NDC 54868-4257-2
Bottles of 60 | NDC 54868-4257-3
Bottles of 100 | NDC 54868-4257-1

300 mg Tablets (NDC 0310-0274) white, capsule-shaped, biconvex, film coated tablets, intagliated with ‘SEROQUEL’ on one side and ‘300’ on the other side, are supplied in

Bottles of 30 | NDC 54868-5484-1
Bottles of 90 | NDC 54868-5484-0

Store at 25ºC (77ºF); excursions permitted to 15-30ºC (59-86ºF) [See USP].

17 PATIENT COUNSELING INFORMATION

[see Medication Guide]

Prescribers or other health professionals should inform patients, their families, and their caregivers about the benefits and risks associated with treatment with SEROQUEL and should counsel them in its appropriate use. A patient Medication Guide about “Antidepressant Medicines, Depression and other Serious Mental Illness, and Suicidal Thoughts or Actions” is available for SEROQUEL. The prescriber or health professional should instruct patients, their families, and their caregivers to read the Medication Guide and should assist them in understanding its contents. Patients should be given the opportunity to discuss the contents of the Medication Guide and to obtain answers to any questions they may have. The complete text of the Medication Guide is reprinted at the end of this document.

Patients should be advised of the following issues and asked to alert their prescriber if these occur while taking SEROQUEL.

Increased Mortality in Elderly Patients with Dementia-Related Psychosis

Patients and caregivers should be advised that elderly patients with dementia-related psychosis treated with atypical antipsychotic drugs are at increased risk of death compared with placebo. Quetiapine is not approved for elderly patients with dementia-related psychosis [see Warnings and Precautions (5.1)].

Clinical Worsening and Suicide Risk

Patients, their families, and their caregivers should be encouraged to be alert to the emergence of anxiety, agitation, panic attacks, insomnia, irritability, hostility, aggressiveness, impulsivity, akathisia (psychomotor restlessness), hypomania, mania, other unusual changes in behavior, worsening of depression, and suicidal ideation, especially early during antidepressant treatment and when the dose is adjusted up or down. Families and caregivers of patients should be advised to look for the emergence of such symptoms on a day-to-day basis, since changes may be abrupt. Such symptoms should be reported to the patient's prescriber or health professional, especially if they are severe, abrupt in onset, or were not part of the patient's presenting symptoms. Symptoms such as these may be associated with an increased risk for suicidal thinking and behavior and indicate a need for very close monitoring and possibly changes in the medication [see Warnings and Precautions (5.2)].

Neuroleptic Malignant Syndrome (NMS)

Patients should be advised to report to their physician any signs or symptoms that may be related to NMS. These may include muscle stiffness and high fever [see Warnings and Precautions (5.3)].

Hyperglycemia and Diabetes Mellitus

Patients should be aware of the symptoms of hyperglycemia (high blood sugar) and diabetes mellitus. Patients who are diagnosed with diabetes, those with risk factors for diabetes, or those that develop these symptoms during treatment should have their blood glucose monitored at the beginning of and periodically during treatment [see Warnings and Precautions (5.4)].

Hyperlipidemia

Patients should be advised that elevations in total cholesterol, LDL–cholesterol and triglycerides and decreases in HDL-cholesterol may occur. Patients should have their lipid profile monitored at the beginning of and periodically during treatment [see Warnings and Precautions (5.5)].

Weight Gain

Patients should be advised that they may experience weight gain. Patients should have their weight monitored regularly [see Warnings and Precautions (5.6)].

Orthostatic Hypotension

Patients should be advised of the risk of orthostatic hypotension (symptoms include feeling dizzy or lightheaded upon standing, which may lead to falls), especially during the period of initial dose titration, and also at times of re-initiating treatment or increases in dose [see Warnings and Precautions (5.8)].

Increased Blood Pressure in Children and Adolescents

Blood pressure should be measured at the beginning of, and periodically during, treatment [see Warnings and Precautions (5.9)].

Leukopenia/Neutropenia

Patients with a pre-existing low WBC or a history of drug induced leukopenia/neutropenia should be advised that they should have their CBC monitored while taking SEROQUEL [see Warnings and Precautions (5.10)].

Interference with Cognitive and Motor Performance

Patients should be advised of the risk of somnolence or sedation (which may lead to falls), especially during the period of initial dose titration. Patients should be cautioned about performing any activity requiring mental alertness, such as operating a motor vehicle (including automobiles) or operating machinery, until they are reasonably certain quetiapine therapy does not affect them adversely. Patients should limit consumption of alcohol during treatment with quetiapine [see Warnings and Precautions (5.17)].

Heat Exposure and Dehydration

Patients should be advised regarding appropriate care in avoiding overheating and dehydration [see Warnings and Precautions (5.19)].

Concomitant Medication

As with other medications, patients should be advised to notify their physicians if they are taking, or plan to take, any prescription or over-the-counter drugs [see Warnings and Precautions (5.22)].

Pregnancy and Nursing

Patients should be advised to notify their physician if they become pregnant or intend to become pregnant during therapy. Patients should be advised not to breast feed if they are taking quetiapine [see Use in Specific Populations (8.1) and (8.3)].

Need for Comprehensive Treatment Program

SEROQUEL is indicated as an integral part of a total treatment program for adolescents with schizophrenia and pediatric bipolar disorder that may include other measures (psychological, educational, and social). Effectiveness and safety of SEROQUEL have not been established in pediatric patients less than 13 years of age for schizophrenia or less than 10 years of age for bipolar mania. Appropriate educational placement is essential and psychosocial intervention is often helpful. The decision to prescribe atypical antipsychotic medication will depend upon the physician’s assessment of the chronicity and severity of the patient’s symptoms.

SPL MEDGUIDE SECTION

MEDICATION GUIDE

SEROQUEL (SER-oh-kwell)

(quetiapine fumarate)

Tablets

Read this Medication Guide before you start taking SEROQUEL and each time you get a refill. There may be new information. This Medication Guide does not take the place of talking to your healthcare provider about your medical condition or treatment.

What is the most important information I should know about SEROQUEL?

SEROQUEL may cause serious side effects, including:

1. Risk of death in the elderly with dementia
2. Risk of suicidal thoughts or actions
3. High blood sugar (hyperglycemia)
4. High fat levels in your blood (increased cholesterol and triglycerides)
5. Weight gain

These serious side effects are described below:

1. Risk of death in the elderly with dementia: Medicines like SEROQUEL can increase the risk of death in elderly people who have memory loss (dementia). SEROQUEL is not approved for treating psychosis in the elderly with dementia.
2. Risk of suicidal thoughts or actions (antidepressant medicines, depression and other serious mental illnesses, and suicidal thoughts or actions):
  Talk to your, or your family member’s, healthcare provider about:
  - all risks and benefits of treatment with antidepressant medicines.
  - all treatment choices for depression or other serious mental illness.

- Antidepressant medications may increase suicidal thoughts or actions in some children, teenagers, and young adults within the first few months of treatment.
- Depression and other serious mental illnesses are the most important causes of suicidal thoughts and actions. Some people may have a particularly high risk of having suicidal thoughts or actions. These include people who have (or have a family history of) depression, bipolar illness (also called manic-depressive illness), or suicidal thoughts or actions.
- How can I watch for and try to prevent suicidal thoughts and actions in myself or a family member?
  - Pay close attention to any changes, especially sudden changes, in mood, behaviors, thoughts, or feelings. This is very important when an antidepressant medicine is started or when the dose is changed.
  - Call the healthcare provider right away to report new or sudden changes in mood, behavior, thoughts, or feelings.
  - Keep all follow-up visits with the healthcare provider as scheduled. Call the healthcare provider between visits as needed, especially if you have concerns about symptoms.

Call a healthcare provider right away if you or your family member has any of the following symptoms, especially if they are new, worse, or worry you:

- thoughts about suicide or dying
- attempts to commit suicide
- new or worse depression
- new or worse anxiety
- feeling very agitated or restless
- panic attacks
- trouble sleeping (insomnia)
- new or worse irritability
- acting aggressive, being angry, or violent
- acting on dangerous impulses
- an extreme increase in activity and talking (mania)
- other unusual changes in behavior or mood

What else do I need to know about antidepressant medicines?

- Never stop an antidepressant medicine without first talking to your healthcare provider. Stopping an antidepressant medicine suddenly can cause other symptoms.
- Antidepressants are medicines used to treat depression and other illnesses. It is important to discuss all the risks of treating depression and also the risks of not treating it. Patients and their families or other caregivers should discuss all treatment choices with the healthcare provider, not just the use of antidepressants.
- Antidepressant medicines have other side effects. Talk to the healthcare provider about the side effects of the medicine prescribed for you or your family member.
- Antidepressant medicines can interact with other medicines. Know all of the medicines that you or your family member take. Keep a list of all medicines to show the healthcare provider. Do not start new medicines without first checking with your healthcare provider.
- Not all antidepressant medicines prescribed for children are FDA approved for use in children. Talk to your child’s healthcare provider for more information.

3. High blood sugar (hyperglycemia): High blood sugar can happen if you have diabetes already or if you have never had diabetes. High blood sugar could lead to:

1. Build up of acid in your blood due to ketones (ketoacidosis)
2. Coma
3. Death

Increases in blood sugar can happen in some people who take SEROQUEL. Extremely high blood sugar can lead to coma or death. If you have diabetes or risk factors for diabetes (such as being overweight or a family history of diabetes) your healthcare provider should check your blood sugar before you start SEROQUEL and during therapy.

Call your doctor if you have any of these symptoms of high blood sugar (hyperglycemia) while taking SEROQUEL:

- feel very thirsty
- need to urinate more than usual
- feel very hungry
- feel weak or tired
- feel sick to your stomach
- feel confused, or your breath smells fruity.

4. High fat levels in your blood (increased cholesterol and triglycerides): High fat levels may happen in people treated with SEROQUEL. You may not have any symptoms, so your doctor may decide to check your cholesterol and triglycerides during your treatment with SEROQUEL.

5. Increase in weight (weight gain): Weight gain is common in people who take SEROQUEL so you and your doctor should check your weight regularly. Talk to your doctor about ways to control weight gain, such as eating a healthy, balanced diet, and exercising.

What is SEROQUEL?

- SEROQUEL is a prescription medicine used to treat schizophrenia in people age 13 or older.
- SEROQUEL is a prescription medicine used to treat bipolar disorder, including:
  - depressive episodes associated with bipolar disorder in adults
  - manic episodes associated with bipolar I disorder alone or with lithium or divalproex in adults
  - long-term treatment of bipolar I disorder with lithium or divalproex in adults
- SEROQUEL is used to treat manic episodes associated with bipolar I disorder in children ages 10 to 17 years old.

SEROQUEL has not been studied in patients younger than 10 years of age.

What should I tell my healthcare provider before taking SEROQUEL?

Before taking SEROQUEL, tell your healthcare provider if you have or have had:

- diabetes or high blood sugar in you or your family: your healthcare provider should check your blood sugar before you start SEROQUEL and also during therapy
- high levels of total cholesterol, triglycerides or LDL-cholesterol or low levels of HDL- cholesterol
- low or high blood pressure
- low white blood cell count
- cataracts
- seizures
- abnormal thyroid tests
- high prolactin levels
- heart problems
- liver problems
- any other medical condition
- pregnancy or plans to become pregnant. It is not known if SEROQUEL will harm your unborn baby
- breast-feeding or plans to breast-feed. SEROQUEL can pass into your breast milk. You and your healthcare provider should decide if you will take SEROQUEL or breast-feed. You should not do both.

Tell the healthcare provider about all the medicines that you take or recently have taken including prescription medicines, nonprescription medicines, herbal supplements and vitamins.

SEROQUEL and other medicines may affect each other causing serious side effects. SEROQUEL may affect the way other medicines work, and other medicines may affect how SEROQUEL works.

Especially tell your healthcare provider if you take or plan to take medicines for:

- depression
- high blood pressure
- Parkinson’s disease
- trouble sleeping
- abnormal heart beats or rhythm

Also tell your healthcare provider if you take or plan to take any of these medicines:

- phenytoin, divalproex or carbamazepine (for epilepsy)
- barbiturates (to help you sleep)
- rifampin (for tuberculosis)
- glucocorticoids (steroids for inflammation)
- thioridazine (an antipsychotic)
- ketoconazole, fluconazole or itraconazole (for fungal infections)
- erythromycin (an antibiotic)
- protease inhibitors (for HIV)

This is not a complete list of medicines that can affect or be affected by SEROQUEL. Your doctor can tell you if it is safe to take SEROQUEL with your other medicines. Do not start or stop any medicines while taking SEROQUEL without talking to your healthcare provider first. Know the medicines you take. Keep a list of your medicines to show your healthcare provider and pharmacist when you get a new medicine.

Tell your healthcare provider if you are having a urine drug screen because SEROQUEL may affect your test results. Tell those giving the test that you are taking SEROQUEL.

How should I take SEROQUEL?

- Take SEROQUEL exactly as your healthcare provider tells you to take it. Do not change the dose yourself.
- Take SEROQUEL by mouth, with or without food.
- If you feel you need to stop SEROQUEL, talk with your healthcare provider first.

If you suddenly stop taking SEROQUEL, you may experience side effects such as trouble sleeping or trouble staying asleep (insomnia), nausea, and vomiting.

- If you miss a dose, take it as soon as you remember. If it is close to the next dose, skip the missed dose. Just take the next dose at your regular time. Do not take 2 doses at the same time unless your healthcare provider tells you to. If you are not sure about your dosing, call your healthcare provider.
- If you take too much SEROQUEL, call your healthcare provider or poison control center at 1-800-222-1222 right away or go to the nearest hospital emergency room.

What should I avoid while taking SEROQUEL?

Do not drive, operate machinery, or do other dangerous activities until you know how SEROQUEL affects you. SEROQUEL may make you drowsy.

- Avoid getting overheated or dehydrated.
  - Do not over-exercise.
  - In hot weather, stay inside in a cool place if possible.
  - Stay out of the sun. Do not wear too much or heavy clothing.
  - Drink plenty of water.
- Do not drink alcohol while taking SEROQUEL. It may make some side effects of SEROQUEL worse.

What are possible side effects of SEROQUEL?

Serious side effects have been reported with SEROQUEL including:

Also, see “What is the most important information I should know about SEROQUEL?” at the beginning of this Medication Guide.

- Neuroleptic malignant syndrome (NMS): NMS is a rare but very serious condition that can happen in people who take antipsychotic medicines, including SEROQUEL. NMS can cause death and must be treated in a hospital. Call your doctor right away if you become severely ill and have some or all of these symptoms:
- high fever
- excessive sweating
- rigid muscles
- confusion
- changes in your breathing, heartbeat, and blood pressure
- Tardive dyskinesia: Tell your healthcare provider about any movements you cannot control in your face, tongue, or other body parts. These may be signs of a serious condition. Tardive dyskinesia may not go away, even if you stop taking SEROQUEL. Tardive dyskinesia may also start after you stop taking SEROQUEL.
- Orthostatic hypotension (decreased blood pressure): lightheadedness or fainting caused by a sudden change in heart rate and blood pressure when rising too quickly from a sitting or lying position.
- Increases in blood pressure: reported in children and teenagers. Your healthcare provider should check blood pressure in children and adolescents before starting SEROQUEL and during therapy.
- Low white blood cell count
- Cataracts
- Seizures
- Abnormal thyroid tests: Your healthcare provider may do blood tests to check your thyroid hormone level.
- Increases in prolactin levels: Your healthcare provider may do blood tests to check your prolactin levels.
- Increases in liver enzymes: Your healthcare provider may do blood tests to check your liver enzyme levels.
- Long lasting and painful erection
- Difficulty swallowing

Common possible side effects with SEROQUEL include:

Adults

- drowsiness
- dry mouth
- dizziness
- weakness
- weight gain
- abdominal pain
- constipation
- sore throat
- sluggishness
- upset stomach
- weight gain
- a sudden drop in blood pressure upon standing
- abnormal liver tests

Children and Adolescents:

- drowsiness
- fatigue
- nausea
- dry mouth
- weight gain
- dizziness
- increased appetite
- vomiting
- rapid heart rate

These are not all the possible side effects of SEROQUEL. For more information, ask your healthcare provider or pharmacist.

Call your healthcare provider for medical advice about side effects. You may report side effects to FDA at 1-800-FDA-1088.

How should I store SEROQUEL?

- Store SEROQUEL at room temperature, between 59°F to 86°F (15°C to 30°C).
- Keep SEROQUEL and all medicines out of the reach of children.

General information about SEROQUEL

Do not take SEROQUEL unless your healthcare provider has prescribed it for you for your condition. Do not share SEROQUEL with other people, even if they have the same condition. It may harm them.

This Medication Guide provides a summary of important information about SEROQUEL. For more information about SEROQUEL, talk with your healthcare provider or pharmacist or call 1-800-236-9933. You can ask your healthcare provider for information about SEROQUEL that is written for health professionals.

What are the ingredients in SEROQUEL?

Active ingredient: quetiapine fumarate

Inactive ingredients: povidone, dibasic dicalcium phosphate dihydrate, microcrystalline cellulose, sodium starch glycolate, lactose monohydrate, magnesium stearate, hypromellose, polyethylene glycol, and titanium dioxide. The 25 mg tablets contain red and yellow ferric oxide. The 100 mg and 400 mg tablets contain only yellow ferric oxide.

The symptoms of Schizophrenia include:

- Having lost touch with reality (psychosis)
- Seeing things that are not there or hearing voices (hallucinations)
- Believing things that are not true (delusions)
- Being suspicious (paranoia).

The symptoms of Bipolar Disorder include:

- General symptoms of bipolar disorder include extreme mood swings, along with other specific symptoms and behaviors. These mood swings, or "episodes," include manic (highs) and depressive (lows).
- Common symptoms of a manic episode include feeling extremely happy, being very irritable, restless, talking too fast and too much, and having more energy and needing less sleep than usual.
- Common symptoms of a depressive episode include feelings of sadness or emptiness, increased tearfulness, a loss of interest in activities you once enjoyed, loss of energy, difficulty concentrating or making decisions, feelings of worthlessness or guilt, changes in sleep or appetite.
- Thoughts of death or suicide.

This Medication Guide has been approved by the U.S. Food and Drug Administration.

SEROQUEL is a trademark of the AstraZeneca group of companies.

©AstraZeneca 2011

Distributed by:

AstraZeneca Pharmaceuticals LP

Wilmington, DE 19850

SIC 35534–XX

Rev. 11/2011

Relabeling and Repackaging by:
Physicians Total Care, Inc.
Tulsa, Oklahoma 74146

PACKAGE LABEL.PRINCIPAL DISPLAY PANEL

SEROQUEL (SER-oh-kwell)
(quetiapine fumarate)
25 mg tablets
50 mg tablets
100 mg tablets
300 mg tablets